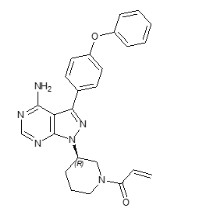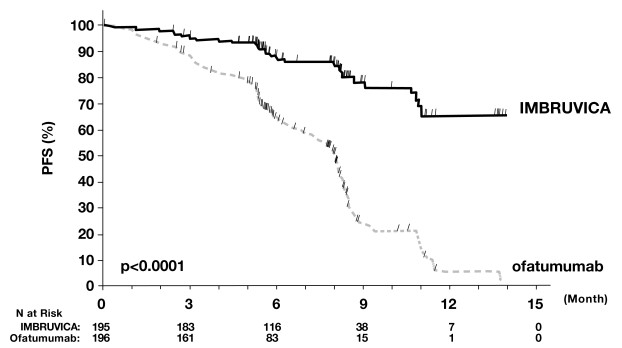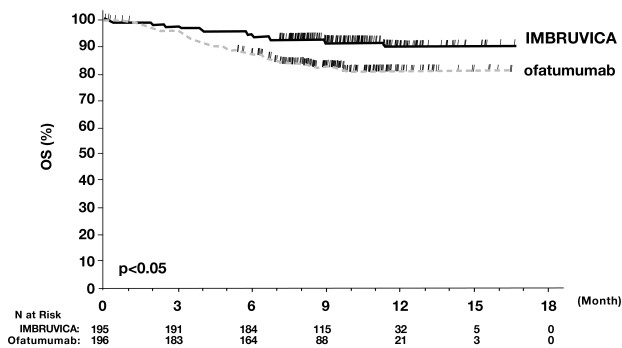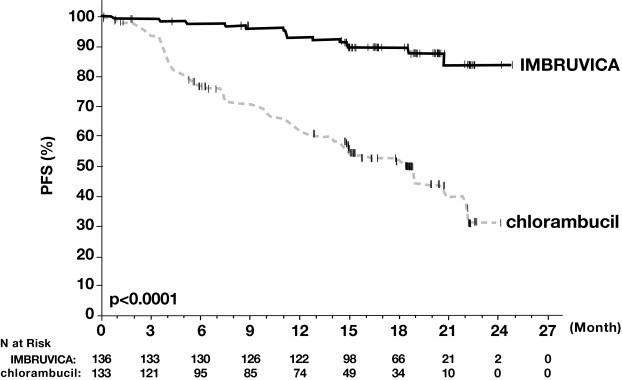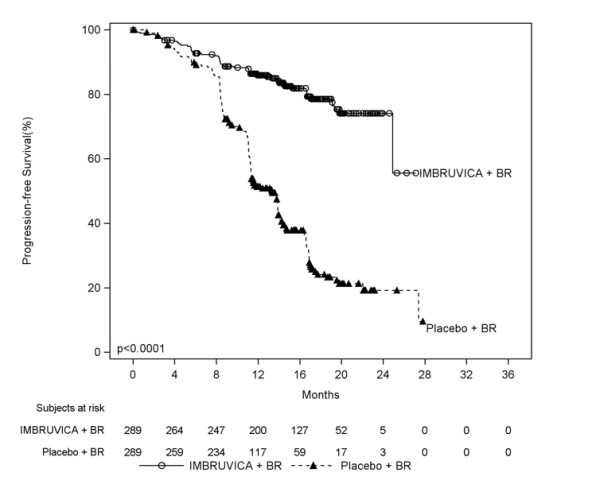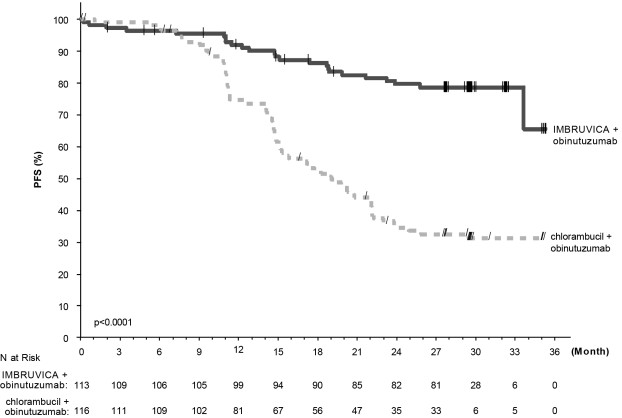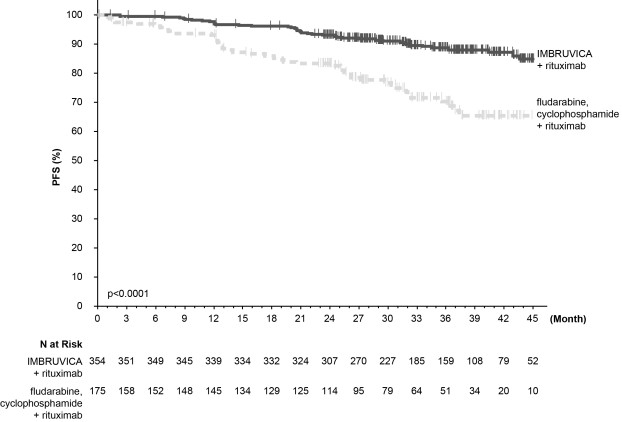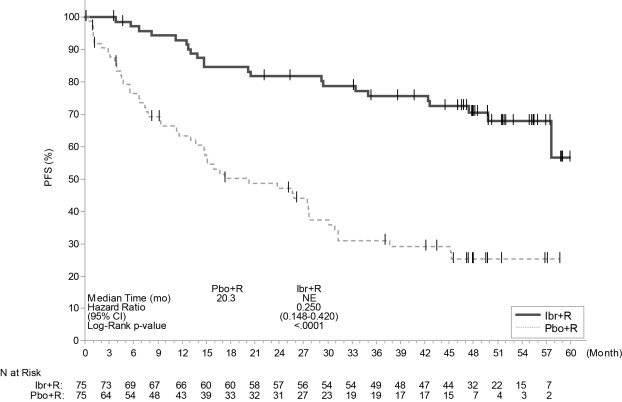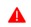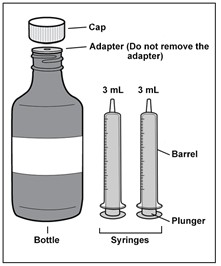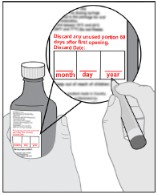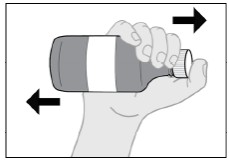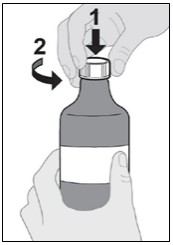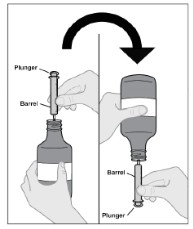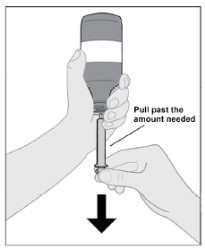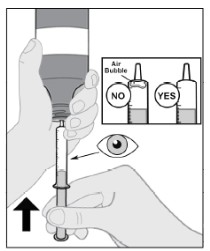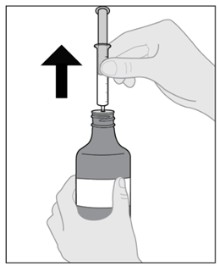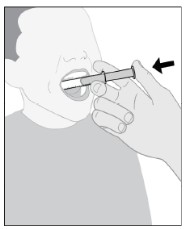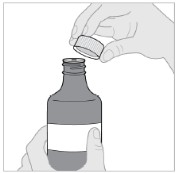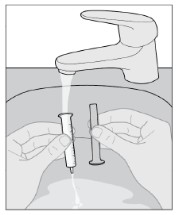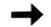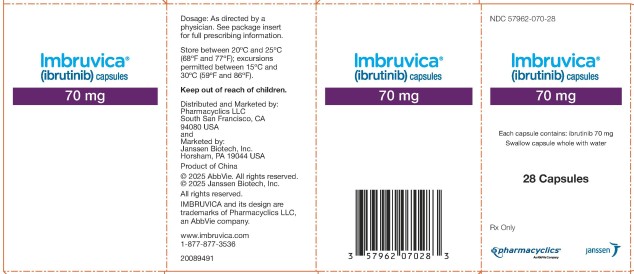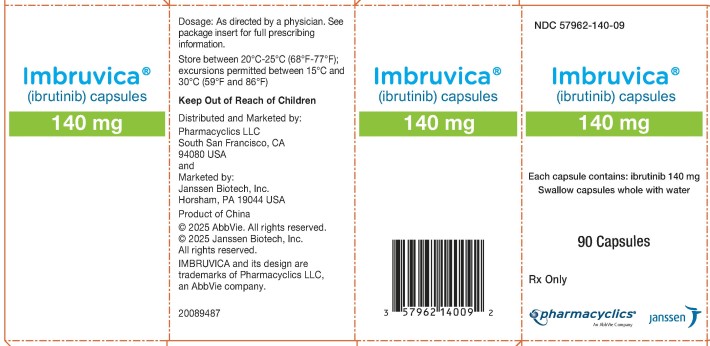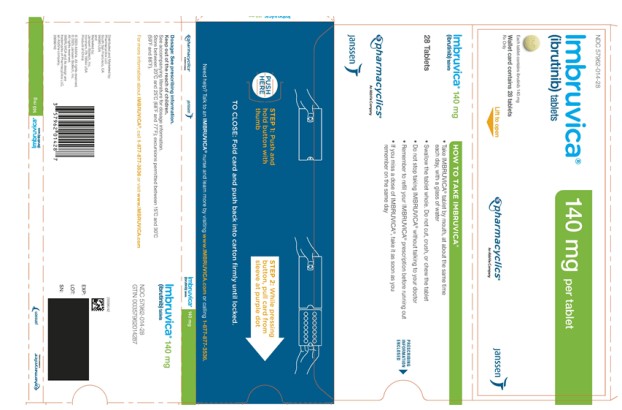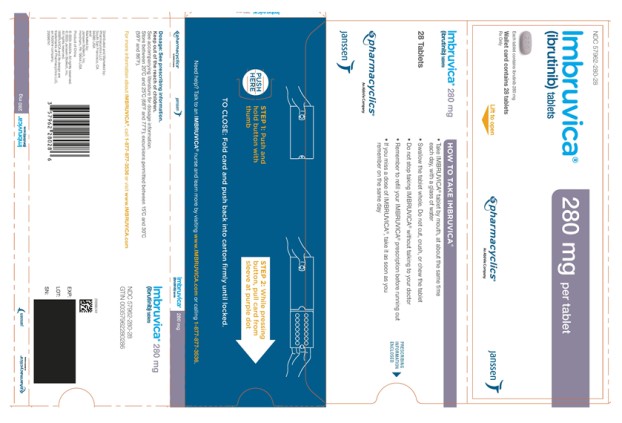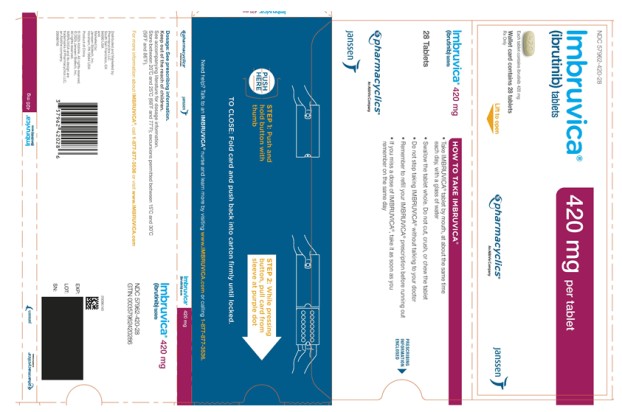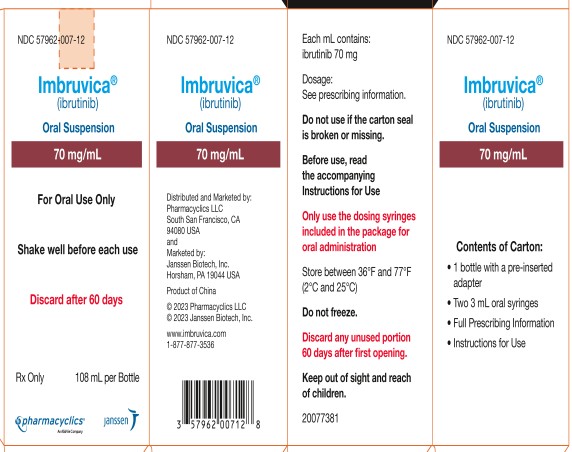 DRUG LABEL: Imbruvica
NDC: 57962-070 | Form: CAPSULE
Manufacturer: Pharmacyclics LLC
Category: prescription | Type: HUMAN PRESCRIPTION DRUG LABEL
Date: 20251021

ACTIVE INGREDIENTS: IBRUTINIB 70 mg/1 1
INACTIVE INGREDIENTS: CROSCARMELLOSE SODIUM; GELATIN; TITANIUM DIOXIDE; FERRIC OXIDE YELLOW

HIGHLIGHTS OF PRESCRIBING INFORMATION

These highlights do not include all the information needed to use IMBRUVICA safely and effectively. See full prescribing information for IMBRUVICA.
IMBRUVICA® (ibrutinib) capsules, for oral use
IMBRUVICA® (ibrutinib) tablets, for oral use
IMBRUVICA® (ibrutinib) oral suspension
Initial U.S. Approval: 2013

1 INDICATIONS AND USAGE

IMBRUVICA is a kinase inhibitor indicated for the treatment of:

- Adult patients with chronic lymphocytic leukemia (CLL)/Small lymphocytic lymphoma (SLL) (1.1).
- Adult patients with chronic lymphocytic leukemia (CLL)/Small lymphocytic lymphoma (SLL) with 17p deletion (1.2).
- Adult patients with Waldenström’s macroglobulinemia (WM) (1.3).
- Adult and pediatric patients age 1 year and older with chronic graft versus host disease (cGVHD) after failure of one or more lines of systemic therapy (1.4).

2 DOSAGE AND ADMINISTRATION

- CLL/SLL and WM: 420 mg taken orally once daily (2.1).
- cGVHD:
  ◦ Patients 12 years and older: 420 mg taken orally once daily (2.1).
  ◦ Patients 1 to less than 12 years of age: 240 mg/m^2 taken orally once daily (up to a dose of 420 mg) (2.1).

Tablets or capsules should be taken orally with a glass of water. Do not open, break, or chew the capsules. Do not cut, crush, or chew the tablets. See full prescribing information for oral suspension administration instructions (2.1).

3 DOSAGE FORMS AND STRENGTHS

Capsules: 70 mg and 140 mg (3)

Tablets: 140 mg, 280 mg, and 420 mg (3)

Oral suspension: 70 mg/mL (3)

4 CONTRAINDICATIONS

None (4)

5 WARNINGS AND PRECAUTIONS

- Hemorrhage: Monitor for bleeding and manage (5.1).
- Infections: Monitor patients for fever and infections, evaluate promptly, and treat (5.2).
- Cardiac Arrhythmias, Cardiac Failure, and Sudden Death: Monitor for symptoms of arrhythmias and cardiac failure and manage (5.3).
- Hypertension: Monitor blood pressure and treat (5.4).
- Cytopenias: Check complete blood counts monthly (5.5).
- Second Primary Malignancies: Other malignancies have occurred in patients, including skin cancers, and other carcinomas (5.6).
- Hepatotoxicity, Including Drug-Induced Liver Injury: Monitor hepatic function throughout treatment (5.7).
- Tumor Lysis Syndrome (TLS): Assess baseline risk and take precautions. Monitor and treat for TLS (5.8).
- Embryo-Fetal Toxicity: Can cause fetal harm. Advise females of reproductive potential of the potential risk to a fetus and to use effective contraception (5.9, 8.1, 8.3).

6 ADVERSE REACTIONS

- The most common (≥30%) adverse reactions in patients with B-cell malignancies are thrombocytopenia, diarrhea, fatigue, musculoskeletal pain, neutropenia, rash, anemia, bruising, and nausea (6).
- The most common (≥20%) adverse reactions in adult or pediatric patients with cGVHD are fatigue, anemia, bruising, diarrhea, thrombocytopenia, musculoskeletal pain, pyrexia, muscle spasms, stomatitis, hemorrhage, nausea, abdominal pain, pneumonia, and headache (6).

To report SUSPECTED ADVERSE REACTIONS, contact AbbVie at 1-800-633-9110 or FDA at 1-800-FDA-1088 or www.fda.gov/medwatch.

7 DRUG INTERACTIONS

- CYP3A Inhibitors: Modify IMBRUVICA dose as described (2.3, 7.1).
- CYP3A Inducers: Avoid coadministration with strong CYP3A inducers (7.2).

8 USE IN SPECIFIC POPULATIONS

- Lactation: Advise not to breastfeed (8.2).
- Hepatic Impairment: Avoid use of IMBRUVICA in patients with severe hepatic impairment. In patients with mild or moderate impairment, reduce IMBRUVICA dose (2.4, 8.6).

FULL PRESCRIBING INFORMATION

1 INDICATIONS AND USAGE

1.1 Chronic Lymphocytic Leukemia/Small Lymphocytic Lymphoma

IMBRUVICA is indicated for the treatment of adult patients with chronic lymphocytic leukemia (CLL)/small lymphocytic lymphoma (SLL).

1.2 Chronic Lymphocytic Leukemia/Small Lymphocytic Lymphoma with 17p deletion

IMBRUVICA is indicated for the treatment of adult patients with chronic lymphocytic leukemia (CLL)/small lymphocytic lymphoma (SLL) with 17p deletion.

1.3 Waldenström’s Macroglobulinemia

IMBRUVICA is indicated for the treatment of adult patients with Waldenström’s macroglobulinemia (WM).

1.4 Chronic Graft versus Host Disease

IMBRUVICA is indicated for the treatment of adult and pediatric patients age 1 year and older with chronic graft-versus-host disease (cGVHD) after failure of one or more lines of systemic therapy.

2 DOSAGE AND ADMINISTRATION

2.1 Recommended Dosage

Chronic Lymphocytic Leukemia/Small Lymphocytic Lymphoma and Waldenström’s Macroglobulinemia

The recommended dosage of IMBRUVICA for CLL/SLL and WM is 420 mg orally once daily until disease progression or unacceptable toxicity.

For CLL/SLL, IMBRUVICA can be administered as a single agent, in combination with rituximab or obinutuzumab, or in combination with bendamustine and rituximab (BR).

For WM, IMBRUVICA can be administered as a single agent or in combination with rituximab.

When administering IMBRUVICA in combination with rituximab or obinutuzumab, consider administering IMBRUVICA prior to rituximab or obinutuzumab when given on the same day.

Chronic Graft versus Host Disease

The recommended dosage of IMBRUVICA for patients age 12 years and older with cGVHD is 420 mg orally once daily, and for patients 1 to less than 12 years of age with cGVHD is 240 mg/m^2 orally once daily (up to a dose of 420 mg), until cGVHD progression, recurrence of an underlying malignancy, or unacceptable toxicity. When a patient no longer requires therapy for the treatment of cGVHD, IMBRUVICA should be discontinued considering the medical assessment of the individual patient.

Table 1: Recommended dosage based on body surface area (BSA) for patients 1 to less than 12 years of age using either IMBRUVICA capsules/tablets or oral suspension
 | Recommended dose to achieve 240 mg/m^2
BSA* (m^2) Range | Dose (mg) of IMBRUVICA Capsules/Tablets to Administer | Volume (mL) of IMBRUVICA Oral Suspension (70 mg/mL) to Administer
> 0.3 to 0.4 | - | 1.2 mL
> 0.4 to 0.5 | - | 1.5 mL
> 0.5 to 0.6 | - | 1.9 mL
> 0.6 to 0.7 | - | 2.2 mL
> 0.7 to 0.8 | 210 mg | 2.6 mL
> 0.8 to 0.9 | 210 mg | 2.9 mL
> 0.9 to 1 | 210 mg | 3.3 mL
> 1 to 1.1 | 280 mg | 3.6 mL
> 1.1 to 1.2 | 280 mg | 4 mL
> 1.2 to 1.3 | 280 mg | 4.3 mL
> 1.3 to 1.4 | 350 mg | 4.6 mL
> 1.4 to 1.5 | 350 mg | 5 mL
> 1.5 to 1.6 | 350 mg | 5.3 mL
> 1.6 | 420 mg | 6 mL

*BSA = body surface area.

Administration

Administer IMBRUVICA at approximately the same time each day.

Swallow tablets or capsules whole with a glass of water. Do not open, break, or chew the capsules. Do not cut, crush, or chew the tablets.

Follow Instructions for Use for further administration details of IMBRUVICA oral suspension.

If a dose of IMBRUVICA is not taken at the scheduled time, it can be taken as soon as possible on the same day with a return to the normal schedule the following day. Do not take extra doses of IMBRUVICA to make up for the missed dose.

2.2 Dosage Modifications for Adverse Reactions

For adverse reactions listed in Table 2, interrupt IMBRUVICA therapy. Once the adverse reaction has improved to Grade 1 or baseline (recovery), follow the recommended dosage modifications (see Table 2).

Table 2: Recommended Dosage Modifications for Adverse Reactions
Adverse Reactiona,b | Occurrence | Dose Modification for CLL/SLL, WM, and Patients 12 Years or older with cGVHD After Recovery Starting Dose = 420 mg | Dose Modification for Patients 1 Year to less than 12 Years with cGVHD After Recovery Starting Dose = 240 mg/m^2
Grade 2 cardiac failure | First | Restart at 280 mg dailyc | Restart at 160 mg/m^2 dailyc
 | Second | Restart at 140 mg dailyc | Restart at 80 mg/m^2 dailyc
 | Third | Discontinue IMBRUVICA | Discontinue IMBRUVICA
Grade 3 cardiac arrhythmias | First | Restart at 280 mg dailyc | Restart at 160 mg/m^2 dailyc
 | Second | Discontinue IMBRUVICA | Discontinue IMBRUVICA
Grade 3 or 4 cardiac failure Grade 4 cardiac arrhythmias | First | Discontinue IMBRUVICA | Discontinue IMBRUVICA
Other Grade 3 or 4 non-hematological toxicitiesd Grade 3 or 4 neutropenia with infection or fever Grade 4 hematological toxicities | First | Restart at 280 mg daily | Restart at 160 mg/m^2 dailyc
 | Second | Restart at 140 mg daily | Restart at 80 mg/m^2 dailyc
 | Third | Discontinue IMBRUVICA | Discontinue IMBRUVICA

a [see Warnings and Precautions (5)].

b Grading based on National Cancer Institute-Common Terminology Criteria for Adverse Events (NCI-CTCAE) criteria, or International Workshop on Chronic Lymphocytic Leukemia (iwCLL) criteria for hematologic toxicities in CLL/SLL.

c Evaluate the benefit-risk before resuming treatment.

d For Grade 4 non-hematologic toxicities, evaluate the benefit-risk before resuming treatment.

Table 3: Recommended dosage modifications based on BSA using either IMBRUVICA capsules/tablets or oral suspension
 | Recommended dose to achieve 160 mg/m^2 |  | Recommended dose to achieve 80 mg/m^2
BSA* (m^2) Range | Dose (mg) of IMBRUVICA Capsules/Tablets to Administer | Volume (mL) of IMBRUVICA Oral Suspension (70 mg/mL) to Administer | Dose (mg) of IMBRUVICA Capsules/Tablets to Administer | Volume (mL) of IMBRUVICA Oral Suspension (70 mg/mL) to Administer
> 0.3 to 0.4 | - | 0.8 mL | - | 0.4 mL
> 0.4 to 0.5 | - | 1 mL | - | 0.5 mL
> 0.5 to 0.6 | - | 1.3 mL | - | 0.6 mL
> 0.6 to 0.7 | - | 1.5 mL | - | 0.7 mL
> 0.7 to 0.8 | 140 mg | 1.7 mL | 70 mg | 0.9 mL
> 0.8 to 0.9 | 140 mg | 1.9 mL | 70 mg | 1 mL
> 0.9 to 1 | 140 mg | 2.2 mL | 70 mg | 1.1 mL
> 1 to 1.1 | 140 mg | 2.4 mL | 70 mg | 1.2 mL
> 1.1 to 1.2 | 210 mg | 2.6 mL | - | 1.3 mL
> 1.2 to 1.3 | 210 mg | 2.9 mL | - | 1.4 mL
> 1.3 to 1.4 | 210 mg | 3.1 mL | - | 1.5 mL
> 1.4 to 1.5 | 210 mg | 3.3 mL | 140 mg | 1.7 mL
> 1.5 to 1.6 | 280 mg | 3.5 mL | 140 mg | 1.8 mL
> 1.6 | 280 mg | 4 mL | 140 mg | 2 mL

*BSA = body surface area.

2.3 Dosage Modifications for Use with CYP3A Inhibitors

Recommended dosage modifications are described below [see Drug Interactions (7.1)]:

Table 4: Recommended Dosage Modifications for Use with CYP3A Inhibitors
Patient Population | Coadministered Drug | Recommended IMBRUVICA Dosage
B-cell Malignancies | - Moderate CYP3A inhibitor | 280 mg once daily Modify dose as recommended [see Dosage and Administration (2.2)].
 | - Voriconazole 200 mg twice daily - Posaconazole suspension 100 mg once daily, 100 mg twice daily, or 200 mg twice daily | 140 mg once daily Modify dose as recommended [see Dosage and Administration (2.2)].
 | - Posaconazole suspension 200 mg three times daily or 400 mg twice daily - Posaconazole intravenously 300 mg once daily - Posaconazole delayed-release tablets 300 mg once daily | 70 mg once daily Interrupt dose as recommended [see Dosage and Administration (2.2)].
 | - Other strong CYP3A inhibitors | Avoid concomitant use. If these inhibitors will be used short-term (such as anti-infectives for seven days or less), interrupt IMBRUVICA.
Patients 12 years and older with cGVHD | - Moderate CYP3A inhibitor | 420 mg once daily Modify dose as recommended [see Dosage and Administration (2.2)].
 | - Voriconazole 200 mg twice daily - Posaconazole suspension 100 mg once daily, 100 mg twice daily, or 200 mg twice daily | 280 mg once daily Modify dose as recommended [see Dosage and Administration (2.2)].
 | - Posaconazole suspension 200 mg three times daily or 400 mg twice daily - Posaconazole intravenously 300 mg once daily - Posaconazole delayed-release tablets 300 mg once daily | 140 mg once daily Interrupt dose as recommended [see Dosage and Administration (2.2)].
 | - Other strong CYP3A inhibitors | Avoid concomitant use. If these inhibitors will be used short-term (such as anti-infectives for seven days or less), interrupt IMBRUVICA.
Patients 1 year to less than 12 years of age with cGVHD | - Moderate CYP3A inhibitors | 240 mg/m^2 once daily Modify dose as recommended [see Dosage and Administration (2.2)].
 | - Voriconazole for suspension 9 mg/kg (maximum dose: 350 mg) twice daily | 160 mg/m^2 once daily
 | - Posaconazole at any dosage | 80 mg/m^2 once daily
 | - Other strong CYP3A inhibitors | Avoid concomitant use. If these inhibitors will be used short-term (such as anti-infectives for seven days or less), interrupt IMBRUVICA.

After discontinuation of a CYP3A inhibitor, resume previous dose of IMBRUVICA [see Dosage and Administration (2.1), Drug Interactions (7.1)].

2.4 Dosage Modifications for Use in Hepatic Impairment

Adult Patients with B-cell Malignancies

The recommended dosage is 140 mg daily for patients with mild hepatic impairment (Child-Pugh class A).

The recommended dosage is 70 mg daily for patients with moderate hepatic impairment (Child-Pugh class B).

Avoid the use of IMBRUVICA in patients with severe hepatic impairment (Child-Pugh class C) [see Use in Specific Populations (8.6), Clinical Pharmacology (12.3)].

Patients with cGVHD

The recommended dosage is 140 mg daily for patients 12 years of age and older with total bilirubin level >1.5 to 3 x upper limit of normal (ULN) (unless of non-hepatic origin or due to Gilbert’s syndrome).

The recommended dosage is 80 mg/m^2 daily for patients 1 to less than 12 years of age with total bilirubin level >1.5 to 3 x ULN (unless of non-hepatic origin or due to Gilbert’s syndrome).

Avoid the use of IMBRUVICA in these patients with total bilirubin level > 3 x ULN (unless of non-hepatic origin or due to Gilbert’s syndrome) [see Use in Specific Populations (8.6), Clinical Pharmacology (12.3)].

3 DOSAGE FORMS AND STRENGTHS

Capsules:

Each 70 mg capsule is a yellow, opaque capsule marked with “ibr 70 mg” in black ink.

Each 140 mg capsule is a white, opaque capsule marked with “ibr 140 mg” in black ink.

Tablets:

Each 140 mg tablet is a yellow green to green round tablet debossed with “ibr” on one side and “140” on the other side.

Each 280 mg tablet is a purple oblong tablet debossed with “ibr” on one side and “280” on the other side.

Each 420 mg tablet is a yellow green to green oblong tablet debossed with “ibr” on one side and “420” on the other side.

Oral Suspension:

70 mg/mL, white to off-white suspension.

4 CONTRAINDICATIONS

None

5 WARNINGS AND PRECAUTIONS

5.1 Hemorrhage

Fatal bleeding events have occurred in patients who received IMBRUVICA. Major hemorrhage (≥ Grade 3, serious, or any central nervous system events; e.g., intracranial hemorrhage [including subdural hematoma], gastrointestinal bleeding, hematuria, and post procedural hemorrhage) occurred in 4.2% of patients, with fatalities occurring in 0.4% of 2,838 patients who received IMBRUVICA in 27 clinical trials. Bleeding events of any grade including bruising and petechiae occurred in 39%, and excluding bruising and petechiae occurred in 23% of patients who received IMBRUVICA, respectively [see Adverse Reactions (6.1)].

The mechanism for the bleeding events is not well understood.

Use of either anticoagulant or antiplatelet agents concomitantly with IMBRUVICA increases the risk of major hemorrhage. Across clinical trials, 3.1% of 2,838 patients who received IMBRUVICA without antiplatelet or anticoagulant therapy experienced major hemorrhage. The addition of antiplatelet therapy with or without anticoagulant therapy increased this percentage to 4.4%, and the addition of anticoagulant therapy with or without antiplatelet therapy increased this percentage to 6.1%. Consider the risks and benefits of anticoagulant or antiplatelet therapy when co-administered with IMBRUVICA. Monitor for signs and symptoms of bleeding.

Consider the benefit-risk of withholding IMBRUVICA for at least 3 to 7 days pre- and post-surgery depending upon the type of surgery and the risk of bleeding [see Clinical Studies (14)].

5.2 Infections

Fatal and non-fatal infections (including bacterial, viral, or fungal) have occurred with IMBRUVICA therapy. Grade 3 or greater infections occurred in 21% of 1,476 patients with B-cell malignancies who received IMBRUVICA in clinical trials [see Adverse Reactions (6.1, 6.2)]. Cases of progressive multifocal leukoencephalopathy (PML) and Pneumocystis jirovecii pneumonia (PJP) have occurred in patients treated with IMBRUVICA. Consider prophylaxis according to standard of care in patients who are at increased risk for opportunistic infections. Monitor and evaluate patients for fever and infections and treat appropriately.

5.3 Cardiac Arrhythmias, Cardiac Failure, and Sudden Death

Fatal and serious cardiac arrhythmias and cardiac failure have occurred with IMBRUVICA. Deaths due to cardiac causes or sudden deaths occurred in 1% of 4,896 patients who received IMBRUVICA in clinical trials, including in patients who received IMBRUVICA in unapproved monotherapy or combination regimens. These adverse reactions occurred in patients with and without preexisting hypertension or cardiac comorbidities. Patients with cardiac comorbidities may be at greater risk of these events.

Grade 3 or greater ventricular tachyarrhythmias were reported in 0.2%, Grade 3 or greater atrial fibrillation and atrial flutter were reported in 3.7%, and Grade 3 or greater cardiac failure was reported in 1.3% of 4,896 patients who received IMBRUVICA in clinical trials, including in patients who received IMBRUVICA in unapproved monotherapy or combination regimens. These events have occurred particularly in patients with cardiac risk factors including hypertension and diabetes mellitus, a previous history of cardiac arrhythmias, and in patients with acute infections [see Adverse Reactions (6.1)].

Evaluate cardiac history and function at baseline, and monitor patients for cardiac arrhythmias and cardiac function. Obtain further evaluation (e.g., ECG, echocardiogram) as indicated for patients who develop symptoms of arrhythmia (e.g., palpitations, lightheadedness, syncope, chest pain), new onset dyspnea, or other cardiovascular concerns. Manage cardiac arrhythmias and cardiac failure appropriately, follow dose modification guidelines [see Dosage and Administration (2.2)], and consider the risks and benefits of continued IMBRUVICA treatment.

5.4 Hypertension

Hypertension occurred in 19% of 1,476 patients with B-cell malignancies who received IMBRUVICA in clinical trials. Grade 3 or greater hypertension occurred in 8% of patients [see Adverse Reactions (6.1)]. Based on data from a subset of these patients (N=1,124), the median time to onset was 5.9 months (range, 0 to 24 months). In a long-term safety analysis over 5 years of 1,284 patients with B-cell malignancies treated for a median of 36 months (range, 0 to 98 months), the cumulative rate of hypertension increased over time. The prevalence for Grade 3 or greater hypertension was 4% (year 0-1), 7% (year 1-2), 9% (year 2-3), 9% (year 3-4), and 9% (year 4-5); the overall incidence for the 5-year period was 11%.

Monitor blood pressure in patients treated with IMBRUVICA, initiate or adjust anti-hypertensive medication throughout treatment with IMBRUVICA as appropriate, and follow dosage modification guidelines for Grade 3 or higher hypertension [see Dosage and Administration (2.2)].

5.5 Cytopenias

In 645 patients with B-cell malignancies who received IMBRUVICA as a single agent, grade 3 or 4 neutropenia occurred in 23% of patients, grade 3 or 4 thrombocytopenia in 8% and grade 3 or 4 anemia in 2.8%, based on laboratory measurements [see Adverse Reactions (6.1)].

Monitor complete blood counts monthly.

5.6 Second Primary Malignancies

Other malignancies (10%), including non-skin carcinomas (3.9%), occurred among the 1,476 patients with B-cell malignancies who received IMBRUVICA in clinical trials [see Adverse Reactions (6.1)]. The most frequent second primary malignancy was non-melanoma skin cancer (6%).

5.7 Hepatotoxicity, Including Drug-Induced Liver Injury

Hepatotoxicity, including severe, life-threatening, and potentially fatal cases of drug-induced liver injury (DILI), has occurred in patients treated with Bruton tyrosine kinase inhibitors, including IMBRUVICA.

Evaluate bilirubin and transaminases at baseline and throughout treatment with IMBRUVICA. For patients who develop abnormal liver tests after IMBRUVICA, monitor more frequently for liver test abnormalities and clinical signs and symptoms of hepatic toxicity. If DILI is suspected, withhold IMBRUVICA. Upon confirmation of DILI, discontinue IMBRUVICA.

5.8 Tumor Lysis Syndrome

Tumor lysis syndrome has been infrequently reported with IMBRUVICA [see Adverse Reactions (6.2)]. Assess the baseline risk (e.g., high tumor burden) and take appropriate precautions. Monitor patients closely and treat as appropriate.

5.9 Embryo-Fetal Toxicity

Based on findings in animals, IMBRUVICA can cause fetal harm when administered to a pregnant woman. Administration of ibrutinib to pregnant rats and rabbits during the period of organogenesis caused embryo-fetal toxicity including malformations at exposures that were 3-20 times higher than those reported in patients with hematologic malignancies. Advise pregnant women of the potential risk to a fetus. Advise females of reproductive potential to use effective contraception during treatment with IMBRUVICA and for 1 month after the last dose. [see Use in Specific Populations (8.1)].

6 ADVERSE REACTIONS

The following clinically significant adverse reactions are described elsewhere in the labeling:

- Hemorrhage [see Warnings and Precautions (5.1)]
- Infections [see Warnings and Precautions (5.2)]
- Cardiac Arrhythmias, Cardiac Failure, and Sudden Death [see Warnings and Precautions (5.3)]
- Hypertension [see Warnings and Precautions (5.4)]
- Cytopenias [see Warnings and Precautions (5.5)]
- Second Primary Malignancies [see Warnings and Precautions (5.6)]
- Hepatotoxicity, including DILI [see Warnings and Precautions (5.7)]
- Tumor Lysis Syndrome [see Warnings and Precautions (5.8)]

6.1 Clinical Trials Experience

Because clinical trials are conducted under widely variable conditions, adverse reaction rates observed in clinical trials of a drug cannot be directly compared with rates of clinical trials of another drug and may not reflect the rates observed in practice.

Unless otherwise specified, the pooled safety population described in the WARNINGS AND PRECAUTIONS reflects exposure to IMBRUVICA in 6 trials. IMBRUVICA was administered as a single agent at 420 mg orally once daily (475 patients), as a single agent at 560 mg orally once daily [1.3 times the recommended adult dosage (174 patients)], and in combination with other drugs at 420 mg orally once daily (827 patients) in patients with B-cell malignancies. In this pooled safety population of 1,476 patients, 87% were exposed for 6 months or longer and 68% were exposed for greater than one year. The most common adverse reactions (≥ 30%) were thrombocytopenia, diarrhea, fatigue, musculoskeletal pain, neutropenia, rash, anemia, bruising, and nausea.

Certain subsections in the WARNINGS AND PRECAUTIONS include patients who received IMBRUVICA in unapproved monotherapy or combination regimens.

Chronic Lymphocytic Leukemia/Small Lymphocytic Lymphoma

The data described below reflect exposure to IMBRUVICA in one single-arm, open-label clinical trial (Study 1102) and five randomized controlled clinical trials (RESONATE, RESONATE-2, HELIOS, iLLUMINATE, and E1912) in patients with CLL/SLL (n=2,016 total, including n=1,133 patients exposed to IMBRUVICA). In general, patients with creatinine clearance (CLcr) ≤ 30 mL/min, AST or ALT ≥ 2.5 x ULN, or total bilirubin ≥ 1.5 x ULN (unless of non-hepatic origin) were excluded from these trials. In Study E1912, patients with AST or ALT > 3 x ULN or total bilirubin > 2.5 x ULN were excluded. Study 1102 included 51 patients with previously treated CLL/SLL. RESONATE included 386 randomized patients with previously treated CLL or SLL who received single agent IMBRUVICA or ofatumumab. RESONATE-2 included 267 randomized patients with treatment naïve CLL or SLL who were 65 years or older and received single agent IMBRUVICA or chlorambucil. HELIOS included 574 randomized patients with previously treated CLL or SLL who received IMBRUVICA in combination with BR or placebo in combination with BR. iLLUMINATE included 228 randomized patients with treatment naïve CLL/SLL who were 65 years or older or with coexisting medical conditions and received IMBRUVICA in combination with obinutuzumab or chlorambucil in combination with obinutuzumab. E1912 included 510 patients with previously untreated CLL/SLL who were 70 years or younger and received IMBRUVICA in combination with rituximab or received fludarabine, cyclophosphamide, and rituximab (FCR).

The most common adverse reactions in patients with CLL/SLL receiving IMBRUVICA (≥ 30%) were thrombocytopenia, diarrhea, fatigue, musculoskeletal pain, neutropenia, rash, anemia, bruising, and nausea.

Four to 10 percent of patients with CLL/SLL receiving IMBRUVICA discontinued treatment due to adverse reactions. These included pneumonia, hemorrhage, atrial fibrillation, neutropenia, arthralgia, rash, and thrombocytopenia. Adverse reactions leading to dose reduction occurred in approximately 9% of patients.

Study 1102

Adverse reactions and laboratory abnormalities from Study 1102 (N=51) using single agent IMBRUVICA 420 mg daily in patients with previously treated CLL/SLL occurring at a rate of ≥ 10% with a median duration of treatment of 15.6 months are presented in Table 5 and Table 6.

Table 5: Non-Hematologic Adverse Reactions in ≥ 10% of Patients with CLL/SLL (N=51) in Study 1102
Body System | Adverse Reaction | All Grades (%) | Grade 3 or Higher (%)
Gastrointestinal disorders | Diarrhea Constipation Nausea Stomatitis Vomiting Abdominal pain Dyspepsia | 59 22 20 20 18 14 12 | 4 2 2 0 2 0 0
Skin and subcutaneous tissue disorders | Bruising Rash Petechiae | 51 25 16 | 2 0 0
Infections and infestations | Upper respiratory tract infection Sinusitis Skin infection Pneumonia Urinary tract infection | 47 22 16 12 12 | 2 6 6 10 2
General disorders and administration site conditions | Fatigue Pyrexia Peripheral edema Asthenia Chills | 33 24 22 14 12 | 6 2 0 6 0
Musculoskeletal and connective tissue disorders | Musculoskeletal pain Arthralgia Muscle spasms | 25 24 18 | 6 0 2
Respiratory, thoracic and mediastinal disorders | Cough Oropharyngeal pain Dyspnea | 22 14 12 | 0 0 0
Nervous system disorders | Dizziness Headache | 20 18 | 0 2
Vascular disorders | Hypertension | 16 | 8
Metabolism and nutrition disorders | Decreased appetite | 16 | 2
Neoplasms benign, malignant, unspecified | Second malignancies | 10 | 2†

†One patient death due to histiocytic sarcoma.

Table 6: Treatment-Emergent* Hematologic Laboratory Abnormalities in Patients with CLL/SLL (N=51) in Study 1102
 | Percent of Patients (N=51)
 | All Grades (%) | Grade 3 or 4 (%)
Platelets decreased | 69 | 12
Neutrophils decreased | 53 | 26
Hemoglobin decreased | 43 | 0

* Based on laboratory measurements per IWCLL criteria and adverse reactions.

Treatment-emergent Grade 4 thrombocytopenia (8%) and neutropenia (12%) occurred in patients.

RESONATE

Adverse reactions and laboratory abnormalities described below in Table 7 and Table 8 reflect exposure to IMBRUVICA with a median duration of 8.6 months and exposure to ofatumumab with a median of 5.3 months in RESONATE in patients with previously treated CLL/SLL.

Table 7: Adverse Reactions Reported in ≥ 10% of Patients in the IMBRUVICA Treated Arm in Patients with CLL/SLL in RESONATE
Body System Adverse Reaction | IMBRUVICA (N=195) |  | Ofatumumab (N=191)
 | All Grades (%) | Grade 3 or Higher (%) | All Grades (%) | Grade 3 or Higher (%)
Gastrointestinal disorders
Diarrhea | 48 | 4 | 18 | 2
Nausea | 26 | 2 | 18 | 0
Stomatitis* | 17 | 1 | 6 | 1
Constipation | 15 | 0 | 9 | 0
Vomiting | 14 | 0 | 6 | 1
Musculoskeletal and connective tissue disorders
Musculoskeletal pain* | 28 | 2 | 18 | 1
Arthralgia | 17 | 1 | 7 | 0
Muscle spasms | 13 | 0 | 8 | 0
Skin and subcutaneous tissue disorders
Rash* | 24 | 3 | 13 | 0
Petechiae | 14 | 0 | 1 | 0
Bruising* | 12 | 0 | 1 | 0
General disorders and administration site conditions
Pyrexia | 24 | 2 | 15 | 2†
Respiratory, thoracic and mediastinal disorders
Cough | 19 | 0 | 23 | 1
Dyspnea | 12 | 2 | 10 | 1
Infections and infestations
Upper respiratory tract infection | 16 | 1 | 11 | 2†
Pneumonia* | 15 | 12† | 13 | 10†
Sinusitis* | 11 | 1 | 6 | 0
Urinary tract infection | 10 | 4 | 5 | 1
Nervous system disorders
Headache | 14 | 1 | 6 | 0
Dizziness | 11 | 0 | 5 | 0
Injury, poisoning and procedural complications
Contusion | 11 | 0 | 3 | 0
Eye disorders
Vision blurred | 10 | 0 | 3 | 0
The body system and individual ADR terms are sorted in descending frequency order in the IMBRUVICA arm.
* Includes multiple ADR terms.
† Includes 3 events of pneumonia with fatal outcome in each arm, and 1 event of pyrexia and upper respiratory tract infection with a fatal outcome in the ofatumumab arm.

Table 8: Treatment-Emergent Hematologic Laboratory Abnormalities in Patients with CLL/SLL in RESONATE
 | IMBRUVICA (N=195) |  | Ofatumumab (N=191)
 | All Grades (%) | Grade 3 or 4 (%) | All Grades (%) | Grade 3 or 4 (%)
Neutrophils decreased | 51 | 23 | 57 | 26
Platelets decreased | 52 | 5 | 45 | 10
Hemoglobin decreased | 36 | 0 | 21 | 0

Treatment-emergent Grade 4 thrombocytopenia (2% in the IMBRUVICA arm vs 3% in the ofatumumab arm) and neutropenia (8% in the IMBRUVICA arm vs 8% in the ofatumumab arm) occurred in patients.

RESONATE-2

Adverse reactions and laboratory abnormalities described below in Table 9 and Table 10 reflect exposure to IMBRUVICA with a median duration of 17.4 months. The median exposure to chlorambucil was 7.1 months in RESONATE-2.

Table 9: Adverse Reactions Reported in ≥ 10% of Patients in the IMBRUVICA Treated Arm in Patients with CLL/SLL in RESONATE-2
Body System Adverse Reaction | IMBRUVICA (N=135) |  | Chlorambucil (N=132)
 | All Grades (%) | Grade 3 or Higher (%) | All Grades (%) | Grade 3 or Higher (%)
Gastrointestinal disorders
Diarrhea | 42 | 4 | 17 | 0
Nausea | 22 | 1 | 39 | 1
Constipation | 16 | 1 | 16 | 0
Stomatitis* | 14 | 1 | 4 | 1
Vomiting | 13 | 0 | 20 | 1
Abdominal pain | 13 | 3 | 11 | 1
Dyspepsia | 11 | 0 | 2 | 0
Musculoskeletal and connective tissue disorders
Musculoskeletal pain* | 36 | 4 | 20 | 0
Arthralgia | 16 | 1 | 7 | 1
Muscle spasms | 11 | 0 | 5 | 0
General disorders and administration site conditions
Fatigue | 30 | 1 | 38 | 5
Peripheral edema | 19 | 1 | 9 | 0
Pyrexia | 17 | 0 | 14 | 2
Respiratory, thoracic and mediastinal disorders
Cough | 22 | 0 | 15 | 0
Dyspnea | 10 | 1 | 10 | 0
Skin and subcutaneous tissue disorders
Rash* | 21 | 4 | 12 | 2
Bruising* | 19 | 0 | 7 | 0
Eye disorders
Dry eye | 17 | 0 | 5 | 0
Lacrimation increased | 13 | 0 | 6 | 0
Vision blurred | 13 | 0 | 8 | 0
Visual acuity reduced | 11 | 0 | 2 | 0
Infections and infestations
Upper respiratory tract infection | 17 | 2 | 17 | 2
Skin infection* | 15 | 2 | 3 | 1
Pneumonia* | 14 | 8 | 7 | 4
Urinary tract infections | 10 | 1 | 8 | 1
Vascular disorders
Hypertension* | 14 | 4 | 1 | 0
Nervous system disorders
Headache | 12 | 1 | 10 | 2
Dizziness | 11 | 0 | 12 | 1
Investigations
Weight decreased | 10 | 0 | 12 | 0

Subjects with multiple events for a given ADR term are counted once only for each ADR term.

The body system and individual ADR terms are sorted in descending frequency order in the IMBRUVICA arm.

* Includes multiple ADR terms.

Table 10: Treatment-Emergent Hematologic Laboratory Abnormalities in Patients with CLL/SLL in RESONATE-2
 | IMBRUVICA (N=135) |  | Chlorambucil (N=132)
 | All Grades (%) | Grade 3 or 4 (%) | All Grades (%) | Grade 3 or 4 (%)
Neutrophils Decreased | 55 | 28 | 67 | 31
Platelets Decreased | 47 | 7 | 58 | 14
Hemoglobin Decreased | 36 | 0 | 39 | 2

Treatment-emergent Grade 4 thrombocytopenia (1% in the IMBRUVICA arm vs 3% in the chlorambucil arm) and neutropenia (11% in the IMBRUVICA arm vs 12% in the chlorambucil arm) occurred in patients.

HELIOS

Adverse reactions described below in Table 11 reflect exposure to IMBRUVICA + BR with a median duration of 14.7 months and exposure to placebo + BR with a median of 12.8 months in HELIOS in patients with previously treated CLL/SLL.

Table 11: Adverse Reactions Reported in ≥ 10% of Patients and ≥ 2% Greater in the IMBRUVICA Arm in Patients with CLL/SLL in HELIOS
Body System Adverse Reaction | IMBRUVICA + BR (N=287) |  | Placebo + BR (N=287)
 | All Grades (%) | Grade 3 or Higher (%) | All Grades (%) | Grade 3 or Higher (%)
Blood and lymphatic system disorders
Neutropenia* | 66 | 61 | 60 | 56†
Thrombocytopenia* | 34 | 16 | 26 | 16
Gastrointestinal disorders
Diarrhea | 36 | 2 | 23 | 1
Abdominal pain | 12 | 1 | 8 | <1
Skin and subcutaneous tissue disorders
Rash* | 32 | 4 | 25 | 1
Bruising * | 20 | <1 | 8 | <1
Musculoskeletal and connective tissue disorders
Musculoskeletal pain* | 29 | 2 | 20 | 0
Muscle spasms | 12 | <1 | 5 | 0
General disorders and administration site conditions
Pyrexia | 25 | 4 | 22 | 2
Vascular disorders
Hemorrhage* | 19 | 2† | 9 | 1
Hypertension* | 11 | 5 | 5 | 2
Infections and infestations
Bronchitis | 13 | 2 | 10 | 3
Skin infection* | 10 | 3 | 6 | 2
Metabolism and nutrition disorders
Hyperuricemia | 10 | 2 | 6 | 0

The body system and individual ADR terms are sorted in descending frequency order in the IMBRUVICA arm.

* Includes multiple ADR terms.

<1 used for frequency above 0 and below 0.5%.

† Includes 2 events of hemorrhage with fatal outcome in the IMBRUVICA arm and 1 event of neutropenia with a fatal outcome in the placebo + BR arm.

Atrial fibrillation of any grade occurred in 7% of patients treated with IMBRUVICA + BR and 2% of patients treated with placebo + BR. The frequency of Grade 3 and 4 atrial fibrillation was 3% in patients treated with IMBRUVICA + BR and 1% in patients treated with placebo + BR.

iLLUMINATE

Adverse reactions described below in Table 12 reflect exposure to IMBRUVICA + obinutuzumab with a median duration of 29.3 months and exposure to chlorambucil + obinutuzumab with a median of 5.1 months in iLLUMINATE in patients with previously untreated CLL/SLL.

Table 12: Adverse Reactions Reported in ≥ 10% of Patients in the IMBRUVICA Arm in Patients with CLL/SLL in iLLUMINATE
Body System Adverse Reaction | IMBRUVICA + Obinutuzumab (N=113) |  | Chlorambucil + Obinutuzumab (N=115)
 | All Grades (%) | Grade 3 or Higher (%) | All Grades (%) | Grade 3 or Higher (%)
Blood and lymphatic system disorders
Neutropenia* | 48 | 39 | 64 | 48
Thrombocytopenia* | 36 | 19 | 28 | 11
Anemia | 17 | 4 | 25 | 8
Skin and subcutaneous tissue disorders
Rash* | 36 | 3 | 11 | 0
Bruising* | 32 | 3 | 3 | 0
Gastrointestinal disorders
Diarrhea | 34 | 3 | 10 | 0
Constipation | 16 | 0 | 12 | 1
Nausea | 12 | 0 | 30 | 0
Musculoskeletal and connective tissue disorders
Musculoskeletal pain* | 33 | 1 | 23 | 3
Arthralgia | 22 | 1 | 10 | 0
Muscle spasms | 13 | 0 | 6 | 0
Respiratory, thoracic and mediastinal disorders
Cough | 27 | 1 | 12 | 0
Injury, poisoning and procedural complications
Infusion related reaction | 25 | 2 | 58 | 8
Vascular disorders
Hemorrhage* | 25 | 1 | 9 | 0
Hypertension* | 17 | 4 | 4 | 3
General disorders and administration site conditions
Pyrexia | 19 | 2 | 26 | 1
Fatigue | 18 | 0 | 17 | 2
Peripheral edema | 12 | 0 | 7 | 0
Infections and infestations
Pneumonia* | 16 | 9 | 9 | 4†
Upper respiratory tract infection | 14 | 1 | 6 | 0
Skin infection* | 13 | 1 | 3 | 0
Urinary tract infection | 12 | 3 | 7 | 1
Nasopharyngitis | 12 | 0 | 3 | 0
Conjunctivitis | 11 | 0 | 2 | 0
Metabolism and nutrition disorders
Hyperuricemia | 13 | 1 | 0 | 0
Cardiac disorders
Atrial fibrillation | 12 | 5 | 0 | 0
Psychiatric disorders
Insomnia | 12 | 0 | 4 | 0

The body system and individual ADR terms are sorted in descending frequency order in the IMBRUVICA arm.

* Includes multiple ADR terms.

† Includes one event with a fatal outcome.

E1912

Adverse reactions described below in Table 13 reflect exposure to IMBRUVICA + rituximab with a median duration of 34.3 months and exposure to FCR with a median of 4.7 months in E1912 in patients with previously untreated CLL/SLL who were 70 years or younger.

Table 13: Adverse Reactions Reported in ≥ 15% of Patients in the IMBRUVICA Arm in Patients with CLL/SLL in E1912
Body System Adverse Reaction | IMBRUVICA + Rituximab (N=352) |  | Fludarabine + Cyclophosphamide + Rituximab (N=158)
 | All Grades (%) | Grade 3 or Higher (%) | All Grades (%) | Grade 3 or Higher (%)
General disorders and administration site conditions
Fatigue | 80 | 2 | 78 | 3
Peripheral edema | 28 | 1 | 17 | 0
Pyrexia | 27 | 1 | 27 | 1
Pain | 23 | 2 | 8 | 0
Musculoskeletal and connective tissue disorders
Musculoskeletal pain* | 61 | 5 | 35 | 2
Arthralgia | 41 | 5 | 10 | 1
Gastrointestinal disorders
Diarrhea | 53 | 4 | 27 | 1
Nausea | 40 | 1 | 64 | 1
Stomatitis* | 22 | 1 | 8 | 1
Abdominal pain* | 19 | 2 | 10 | 1
Vomiting | 18 | 2 | 28 | 0
Constipation | 17 | 0 | 32 | 0
Skin and subcutaneous tissue disorders
Rash* | 49 | 4 | 29 | 5
Bruising* | 36 | 1 | 4 | 1
Vascular disorders
Hypertension* | 42 | 19 | 22 | 6
Hemorrhage* | 31 | 2 | 8 | 1
Nervous system disorders
Headache | 40 | 1 | 27 | 1
Dizziness | 21 | 1 | 13 | 1
Peripheral neuropathy* | 19 | 1 | 13 | 1
Respiratory, thoracic and mediastinal disorders
Cough | 32 | 0 | 25 | 0
Dyspnea | 22 | 2 | 21 | 1
Infections and infestations
Upper respiratory tract | 29 | 1 | 19 | 2
infection
Skin infection* | 16 | 1 | 3 | 1
Metabolism and nutrition disorders
Hyperuricemia | 19 | 1 | 4 | 0
Decreased appetite | 15 | 0 | 20 | 1
Psychiatric disorders
Insomnia | 16 | 1 | 19 | 1

The body system and individual ADR terms are sorted in descending frequency order in the IMBRUVICA arm.

* Includes multiple ADR terms.

Table 14: Select Laboratory Abnormalities (≥ 15% Any Grade), New or Worsening from Baseline in Patients Receiving IMBRUVICA (E1912)
 | IMBRUVICA + Rituximab (N=352) |  | Fludarabine + Cyclophosphamide + Rituximab (N=158)
 | All Grades (%) | Grade 3 or 4 (%) | All Grades (%) | Grade 3 or 4 (%)
Hematology abnormalities Neutrophils decreased Platelets decreased Hemoglobin decreased | 53 43 26 | 30 7 0 | 70 69 51 | 44 25 2
Chemistry abnormalities Creatinine increased Bilirubin increased AST increased | 38 30 25 | 1 2 3 | 17 15 23 | 1 0 <1

Based on laboratory measurements per IWCLL criteria.

Waldenström’s Macroglobulinemia

The data described below reflect exposure to IMBRUVICA in two single-arm clinical trials (Study 1118 and the INNOVATE monotherapy arm) and one randomized controlled trial (INNOVATE), including a total of 169 patients with WM exposed to IMBRUVICA. Study 1118 included 63 patients with previously treated WM who received single agent IMBRUVICA. INNOVATE included 150 patients with treatment naïve or previously treated WM who received IMBRUVICA or placebo in combination with rituximab. The INNOVATE monotherapy arm included 31 patients with previously treated WM who received IMBRUVICA after failure of prior rituximab-containing therapy.

The most common adverse reactions in Studies 1118 and INNOVATE (≥ 20%) were neutropenia, diarrhea, bruising, thrombocytopenia, hemorrhage, musculoskeletal pain, rash, and nausea.

Five percent of patients receiving IMBRUVICA across Studies 1118 and INNOVATE discontinued treatment due to adverse reactions. The most common adverse reaction leading to discontinuation was atrial fibrillation. Adverse reactions leading to dose reduction occurred in 14% of patients.

Study 1118 and INNOVATE Monotherapy Arm

Adverse reactions and laboratory abnormalities described below in Table 15 and Table 16 reflect exposure to IMBRUVICA with a median duration of 11.7 months in Study 1118 and 33 months in the INNOVATE Monotherapy Arm.

Table 15: Non-Hematologic Adverse Reactions in ≥ 10% in Patients with WM in Study 1118 and the INNOVATE Monotherapy Arm (N=94)
Body System | Adverse Reaction | All Grades (%) | Grade 3 or Higher (%)
Gastrointestinal disorders | Diarrhea Nausea Stomatitis* Constipation Gastroesophageal reflux disease | 38 21 15 12 12 | 2 0 0 1 0
Skin and subcutaneous tissue disorders | Bruising* Rash* | 28 21 | 1 1
Vascular disorders | Hemorrhage* Hypertension* | 28 14 | 0 4
General disorders and administrative site conditions | Fatigue Pyrexia | 18 12 | 2 2
Musculoskeletal and connective tissue disorders | Musculoskeletal pain* Muscle spasms | 21 19 | 0 0
Infections and infestations | Upper respiratory tract infection Skin infection* Sinusitis* Pneumonia* | 19 18 16 13 | 0 3 0 5
Nervous system disorders | Headache Dizziness | 14 13 | 0 0
Respiratory, thoracic and mediastinal disorders | Cough | 13 | 0

The body system and individual ADR preferred terms are sorted in descending frequency order.

* Includes multiple ADR terms.

Table 16: Treatment-Emergent Hematologic Laboratory Abnormalities in Patients with WM in Study 1118 and the INNOVATE Monotherapy Arm (N=94)
 | Percent of Patients (N=94)
 | All Grades (%) | Grade 3 or 4 (%)
Platelets Decreased | 38 | 11
Neutrophils Decreased | 43 | 16
Hemoglobin Decreased | 21 | 6

Treatment-emergent Grade 4 thrombocytopenia (4%) and neutropenia (7%) occurred in patients.

INNOVATE

Adverse reactions described below in Table 17 reflect exposure to IMBRUVICA + R with a median duration of 25.8 months and exposure to placebo + R with a median duration of 15.5 months in patients with treatment naïve or previously treated WM in INNOVATE.

Table 17: Adverse Reactions Reported in ≥ 10% of Patients and ≥ 2% Greater in the IMBRUVICA Arm in Patients with WM in INNOVATE
Body System Adverse Reaction | IMBRUVICA + R (N=75) |  | Placebo + R (N=75)
 | All Grades (%) | Grade 3 or Higher (%) | All Grades (%) | Grade 3 or Higher (%)
Skin and subcutaneous tissue disorders
Bruising* | 37 | 1 | 5 | 0
Rash* | 24 | 1 | 11 | 0
Musculoskeletal and connective tissue disorders
Musculoskeletal pain* | 35 | 4 | 21 | 3
Arthralgia | 24 | 3 | 11 | 1
Muscle spasms | 17 | 0 | 12 | 1
Vascular disorders
Hemorrhage* | 32 | 3 | 17 | 4†
Hypertension* | 20 | 13 | 5 | 4
Gastrointestinal disorders
Diarrhea | 28 | 0 | 15 | 1
Nausea | 21 | 0 | 12 | 0
Dyspepsia | 16 | 0 | 1 | 0
Constipation | 13 | 1 | 11 | 1
Infections and infestations
Pneumonia* | 19 | 13 | 5 | 3
Skin infection* | 17 | 3 | 3 | 0
Urinary tract infection | 13 | 0 | 0 | 0
Bronchitis | 12 | 3 | 7 | 0
Influenza | 12 | 0 | 7 | 1
Viral upper respiratory tract infection | 11 | 0 | 7 | 0
General disorders and administration site conditions
Peripheral edema | 17 | 0 | 12 | 1
Respiratory, thoracic, and mediastinal disorders
Cough | 17 | 0 | 11 | 0
Blood and lymphatic system disorders
Neutropenia* | 16 | 12 | 11 | 4
Cardiac disorders
Atrial fibrillation | 15 | 12 | 3 | 1
Nervous system disorders
Dizziness | 11 | 0 | 7 | 0
Psychiatric disorders
Insomnia | 11 | 0 | 4 | 0
Metabolism and nutrition disorders
Hypokalemia | 11 | 0 | 1 | 1

The body system and individual ADR preferred terms are sorted in descending frequency order.

* Includes multiple ADR terms.

† Includes one event with a fatal outcome.

Grade 3 or 4 infusion related reactions were observed in 1% of patients treated with IR.

Chronic Graft versus Host Disease

Study 1129

The data described below reflect exposure to IMBRUVICA in an open-label clinical trial (Study 1129) that included 42 patients with cGVHD after failure of first line corticosteroid therapy and required additional therapy [see Clinical Studies (14.3)].

The most common adverse reactions in Study 1129 (≥ 20%) were fatigue, bruising, diarrhea, thrombocytopenia, stomatitis, muscle spasms, nausea, hemorrhage, anemia, and pneumonia. Atrial fibrillation occurred in one patient (2%) which was Grade 3.

Twenty-four percent of patients receiving IMBRUVICA in Study 1129 discontinued treatment due to adverse reactions. The most common adverse reactions leading to discontinuation were fatigue and pneumonia. Adverse reactions leading to dose reduction occurred in 26% of patients.

Adverse reactions and laboratory abnormalities described below in Table 18 and Table 19 reflect exposure to IMBRUVICA with a median duration of 4.4 months in Study 1129.

Table 18: Non-Hematologic Adverse Reactions in ≥ 10% of Adult Patients with cGVHD in Study 1129 (N=42)
Body System | Adverse Reaction | All Grades (%) | Grade 3 or Higher (%)
General disorders and administration site conditions | Fatigue Pyrexia Edema peripheral | 57 17 12 | 12 5 0
Skin and subcutaneous tissue disorders | Bruising* Rash* | 40 12 | 0 0
Gastrointestinal disorders | Diarrhea Stomatitis* Nausea Constipation | 36 29 26 12 | 10 2 0 0
Musculoskeletal and connective tissue disorders | Muscle spasms Musculoskeletal pain* | 29 14 | 2 5
Vascular disorders | Hemorrhage* | 26 | 0
Infections and infestations | Pneumonia* Upper respiratory tract infection Sepsis* | 21 19 10 | 14† 0 10
Nervous system disorders | Headache | 17 | 5
Injury, poisoning and procedural complications | Fall | 17 | 0
Respiratory, thoracic and mediastinal disorders | Cough Dyspnea | 14 12 | 0 2
Metabolism and nutrition disorders | Hypokalemia | 12 | 7

The system organ class and individual ADR preferred terms are sorted in descending frequency order.

* Includes multiple ADR terms.

† Includes 2 events with a fatal outcome.

Table 19: Treatment-Emergent Hematologic Laboratory Abnormalities in Adult Patients with cGVHD in Study 1129 (N=42)
 | Percent of Patients (N=42)
 | All Grades (%) | Grade 3 or 4 (%)
Platelets decreased | 33 | 0
Neutrophils decreased | 10 | 10
Hemoglobin decreased | 24 | 2

Treatment-emergent Grade 4 neutropenia occurred in 2% of patients.

iMAGINE

The safety of IMBRUVICA was evaluated in the iMAGINE study, which included 47 pediatric and young adult patients 1 year to less than 22 years of age with cGVHD after failure of one or more lines of systemic therapy. Patients age 12 years and older were treated with IMBRUVICA 420 mg orally once daily, and patients age 1 year to less than 12 years were treated with IMBRUVICA 240 mg/m^2 orally once daily [see Clinical Studies (14.3)]. The median duration of exposure to IMBRUVICA was 7.1 months (range, 0.2 to 25.9 months).

Serious adverse reactions occurred in 64% of patients who received IMBRUVICA. Serious adverse reactions in more than two patients included pneumonia, pyrexia, sepsis, and stomatitis. Fatal adverse reactions occurred in two patients who received IMBRUVICA, including sepsis and acute respiratory distress syndrome (ARDS).

Permanent discontinuation of IMBRUVICA due to an adverse reaction occurred in 23% of patients. Adverse reactions which resulted in permanent discontinuation in at least two patients included hemorrhage. Dose reductions of IMBRUVICA due to an adverse reaction occurred in 19% of patients. Adverse reactions which required dose reduction in at least two patients included stomatitis.

The most common (≥ 20%) adverse reactions, including laboratory abnormalities, were anemia, musculoskeletal pain, pyrexia, diarrhea, pneumonia, abdominal pain, stomatitis, thrombocytopenia, and headache.

Table 20 summarizes the adverse reactions in iMAGINE.

Table 20: Adverse Reactions (≥ 10%) in Patients with Previously Treated cGVHD Who Received IMBRUVICA in iMAGINE
 | IMBRUVICA (N=47)
Body System Adverse Reaction | All Grades (%) | Grade 3 or 4 (%)
General disorders and administration site conditions
Pyrexia | 30 | 11
Musculoskeletal and connective tissue disorders
Musculoskeletal pain* | 30 | 2
Osteonecrosis | 11 | 9
Gastrointestinal disorders
Diarrhea | 28 | 2
Abdominal pain* | 23 | 4
Stomatitis* | 23 | 9
Vomiting | 19 | 2
Nausea | 19 | 4
Infections and infestations
Pneumonia* | 23 | 13
Skin infection* | 17 | 4
Sepsis* | 11 | 9†
Nervous system disorders
Headache | 21 | 2
Skin and subcutaneous tissue disorders
Rash* | 19 | 2
Pruritus | 13 | 0
Petechiae | 13 | 0
Respiratory, thoracic and mediastinal disorders
Cough | 19 | 2
Vascular disorders
Hemorrhage* | 17 | 0
Hypertension* | 11 | 4
Blood and lymphatic system disorders
Hypokalemia | 15 | 6
Hypogammaglobulinemia* | 11 | 0
Cardiac Disorders
Sinus tachycardia | 11 | 0
Investigations
Alanine aminotransferase increased | 11 | 2

The system organ class and individual ADR preferred terms are sorted in descending frequency order.

* Includes multiple ADR terms.

† Includes 1 fatal outcome.

Table 21 summarizes the laboratory abnormalities in iMAGINE.

Table 21: Select Hematologic Laboratory Abnormalities (≥ 10%) That Worsened from Baseline in Patients with Previously Treated cGVHD Who Received IMBRUVICA in iMAGINE
 | IMBRUVICA (N=47)
 | All Grades (%) | Grade 3 or 4 (%)
Hemoglobin decreased | 49 | 13
Platelets decreased | 21 | 4
Neutrophils decreased | 13 | 6

Treatment-emergent Grade 4 neutropenia occurred in 3% of patients.

Additional Important Adverse Reactions

Cardiovascular Events

Data on cardiovascular events are based on randomized controlled trials with IMBRUVICA (n=2,115; median treatment duration of 19.1 months for 1,157 patients treated with IMBRUVICA and 5.3 months for 958 patients in the control arm). The incidence of ventricular tachyarrhythmias (ventricular extrasystoles, ventricular arrhythmias, ventricular fibrillation, ventricular flutter, and ventricular tachycardia) of any grade was 1.0% versus 0.4% and of Grade 3 or greater was 0.3% versus 0% in patients treated with IMBRUVICA compared to patients in the control arm. The incidence of atrial fibrillation and atrial flutter of any grade was 8.4% versus 1.6% and for Grade 3 or greater was 4.0% versus 0.5% in patients treated with IMBRUVICA compared to patients in the control arm. In addition, the incidence of cardiac failure of any grade was 1.7% versus 0.5% and for Grade 3 or greater was 1.2% versus 0.3% in patients treated with IMBRUVICA compared to patients in the control arm.

The incidence of ischemic cerebrovascular events (cerebrovascular accidents, ischemic stroke, cerebral ischemia, and transient ischemic attack) of any grade was 1% versus 0.4% and Grade 3 or greater was 0.5% versus 0.2% in patients treated with IMBRUVICA compared to patients in the control arm, respectively.

Diarrhea

In randomized controlled trials (n=2,115; median treatment duration of 19.1 months for 1,157 patients treated with IMBRUVICA and 5.3 months for 958 patients in the control arm), diarrhea of any grade occurred at a rate of 43% of patients treated with IMBRUVICA compared to 19% of patients in the control arm. Grade 3 diarrhea occurred in 3% versus 1% of IMBRUVICA-treated patients compared to the control arm, respectively. Less than 1% (0.3%) of subjects discontinued IMBRUVICA due to diarrhea compared with 0% in the control arm.

Based on data from 1,605 of these patients, the median time to first onset was 21 days (range, 0 to 708) versus 46 days (range, 0 to 492) for any grade diarrhea and 117 days (range, 3 to 414) versus 194 days (range, 11 to 325) for Grade 3 diarrhea in IMBRUVICA-treated patients compared to the control arm, respectively. Of the patients who reported diarrhea, 85% versus 89% had complete resolution, and 15% versus 11% had not reported resolution at time of analysis in IMBRUVICA-treated patients compared to the control arm, respectively. The median time from onset to resolution in IMBRUVICA-treated subjects was 7 days (range, 1 to 655) versus 4 days (range, 1 to 367) for any grade diarrhea and 7 days (range, 1 to 78) versus 19 days (range, 1 to 56) for Grade 3 diarrhea in IMBRUVICA-treated subjects compared to the control arm, respectively.

Visual Disturbance

In randomized controlled trials (n=2,115; median treatment duration of 19.1 months for 1,157 patients treated with IMBRUVICA and 5.3 months for 958 patients in the control arm), blurred vision and decreased visual acuity of any grade occurred in 11% of patients treated with IMBRUVICA (9% Grade 1, 2% Grade 2, no Grade 3 or higher) compared to 6% in the control arm (5% Grade 1 and < 1% Grade 2 and 3).

Based on data from 1,605 of these patients, the median time to first onset was 91 days (range, 0 to 617) versus 100 days (range, 2 to 477) in IMBRUVICA-treated patients compared to the control arm, respectively. Of the patients who reported visual disturbances, 60% versus 71% had complete resolution and 40% versus 29% had not reported resolution at the time of analysis in IMBRUVICA-treated patients compared to the control arm, respectively. The median time from onset to resolution was 37 days (range, 1 to 457) versus 26 days (range, 1 to 721) in IMBRUVICA-treated subjects compared to the control arm, respectively.

6.2 Postmarketing Experience

The following adverse reactions have been identified during postapproval use of IMBRUVICA. Because these reactions are reported voluntarily from a population of uncertain size, it is not always possible to reliably estimate their frequency or establish a causal relationship to drug exposure.

- Hepatobiliary disorders: hepatic failure including acute and/or fatal events, hepatic cirrhosis, drug-induced liver injury
- Respiratory disorders: interstitial lung disease
- Metabolic and nutrition disorders: tumor lysis syndrome
- Immune system disorders: anaphylactic shock, angioedema, urticaria
- Skin and subcutaneous tissue disorders: Stevens-Johnson Syndrome (SJS), onychoclasis, panniculitis, neutrophilic dermatoses, cutaneous vasculitis
- Infections: hepatitis B reactivation
- Nervous system disorders: peripheral neuropathy
- Eye disorders: uveitis

7 DRUG INTERACTIONS

7.1 Effect of CYP3A Inhibitors on Ibrutinib

The coadministration of IMBRUVICA with a strong or moderate CYP3A inhibitor may increase ibrutinib plasma concentrations [see Clinical Pharmacology (12.3)]. Increased ibrutinib concentrations may increase the risk of drug-related toxicity.

Dose modifications of IMBRUVICA are recommended when used concomitantly with posaconazole, voriconazole and moderate CYP3A inhibitors [see Dosage and Administration (2.3)].

Avoid concomitant use of other strong CYP3A inhibitors. Interrupt IMBRUVICA if these inhibitors will be used short-term (such as anti-infectives for seven days or less) [see Dosage and Administration (2.3)].

Avoid grapefruit and Seville oranges during IMBRUVICA treatment, as these contain strong or moderate inhibitors of CYP3A.

7.2 Effect of CYP3A Inducers on Ibrutinib

The coadministration of IMBRUVICA with strong CYP3A inducers may decrease ibrutinib concentrations. Avoid coadministration with strong CYP3A inducers [see Clinical Pharmacology (12.3)].

8 USE IN SPECIFIC POPULATIONS

8.1 Pregnancy

Risk Summary

IMBRUVICA can cause fetal harm based on findings from animal studies. There are no available data on IMBRUVICA use in pregnant women to inform a drug-associated risk of major birth defects and miscarriage. In animal reproduction studies, administration of ibrutinib to pregnant rats and rabbits during the period of organogenesis at exposures up to 3-20 times the clinical dose of 420 mg daily produced embryofetal toxicity including structural abnormalities (see Data). Advise pregnant women of the potential risk to a fetus.

All pregnancies have a background risk of birth defect, loss, or other adverse outcomes. The estimated background risk of major birth defects and miscarriage for the indicated population is unknown. In the U.S. general population, the estimated background risk of major birth defects and miscarriage in clinically recognized pregnancies is 2-4% and 15-20%, respectively.

Data

Animal Data

Ibrutinib was administered orally to pregnant rats during the period of organogenesis at doses of 10, 40 and 80 mg/kg/day. Ibrutinib at a dose of 80 mg/kg/day was associated with visceral malformations (heart and major vessels) and increased resorptions and post-implantation loss. The dose of 80 mg/kg/day in rats is approximately 20 times the exposure in patients with CLL/SLL or WM administered a dose of 420 mg daily. Ibrutinib at doses of 40 mg/kg/day or greater was associated with decreased fetal weights. The dose of 40 mg/kg/day in rats is approximately 8 times the exposure (AUC) in patients administered a dose of 420 mg daily.

Ibrutinib was also administered orally to pregnant rabbits during the period of organogenesis at doses of 5, 15, and 45 mg/kg/day. Ibrutinib at a dose of 15 mg/kg/day or greater was associated with skeletal variations (fused sternebrae) and ibrutinib at a dose of 45 mg/kg/day was associated with increased resorptions and post-implantation loss. The dose of 15 mg/kg/day in rabbits is approximately 2.8 times the exposure in patients with CLL/SLL or WM administered a dose of 420 mg daily.

8.2 Lactation

Risk Summary

There is no information regarding the presence of ibrutinib or its metabolites in human milk, the effects on the breastfed child, or the effects on milk production. Because of the potential for serious adverse reactions in the breastfed child, advise women not to breastfeed during treatment with IMBRUVICA and for 1 week after the last dose.

8.3 Females and Males of Reproductive Potential

IMBRUVICA can cause fetal harm when administered to pregnant women [see Use in Specific Populations (8.1)].

Pregnancy Testing

Verify pregnancy status in females of reproductive potential prior to initiating IMBRUVICA.

Contraception

Females

Advise females of reproductive potential to use effective contraception during treatment with IMBRUVICA and for 1 month after the last dose.

Males

Advise males with female partners of reproductive potential to use effective contraception during treatment with IMBRUVICA and for 1 month following the last dose.

8.4 Pediatric Use

Chronic GVHD

The safety and effectiveness of IMBRUVICA have been established for treatment of cGVHD after failure of one or more lines of systemic therapy in pediatric patients 1 year of age and older.

Use of IMBRUVICA for this indication is supported by evidence from iMAGINE, a study which included pediatric patients age 1 year and older with previously treated cGVHD, including patients in the following age groups: one patient 1 year to less than 2 years of age, 20 patients 2 years to less than 12 years of age, and 19 patients 12 years to less than 17 years of age. Additional supportive efficacy data was provided from Study 1129 in adults [see Adverse Reactions (6.1), Clinical Pharmacology (12.3), and Clinical Studies (14.3)].

The recommended dosage of IMBRUVICA in patients age 12 years and older is the same as that in adults, and the recommended dosage in patients age 1 year to less than 12 years old is based on body-surface area (BSA) [see Dosage and Administration (2.1)].

The safety and effectiveness of IMBRUVICA have not been established for this indication in pediatric patients less than 1 year of age.

Mature B-cell Non-Hodgkin Lymphoma

The safety and effectiveness of IMBRUVICA in combination with chemoimmunotherapy were assessed but have not been established based on an open-label, randomized study (NCT02703272) in 35 patients, which included 26 pediatric patients age 5 to less than 17 years, with previously treated mature B-cell non-Hodgkin lymphoma. The study was stopped for futility. In the randomized population, major hemorrhage and discontinuation of chemoimmunotherapy due to adverse reactions occurred more frequently in the ibrutinib plus chemoimmunotherapy arm compared to the chemoimmunotherapy alone arm.

CLL/SLL, CLL/SLL with 17p deletion, WM

The safety and effectiveness of IMBRUVICA in pediatric patients have not been established in CLL/SLL, CLL/SLL with 17p deletion, or WM.

8.5 Geriatric Use

Of 992 patients in clinical studies of IMBRUVICA for B-cell malignancies or cGVHD, 62% were ≥ 65 years of age, while 22% were ≥ 75 years of age [see Clinical Studies (14.1, 14.2, 14.3)]. No overall differences in effectiveness were observed between younger and older patients. Anemia (all grades), pneumonia (Grade 3 or higher), thrombocytopenia, hypertension, and atrial fibrillation occurred more frequently among older patients treated with IMBRUVICA [see Adverse Reactions (6.1)].

8.6 Hepatic Impairment

Adult Patients with B-cell Malignancies

Avoid use of IMBRUVICA in patients with severe hepatic impairment (Child-Pugh class C). The safety of IMBRUVICA has not been evaluated in patients with mild to severe hepatic impairment by Child-Pugh criteria.

Reduce the recommended dose when administering IMBRUVICA to patients with mild or moderate hepatic impairment (Child-Pugh class A and B). Monitor patients more frequently for adverse reactions of IMBRUVICA [see Dosage and Administration (2.4), Clinical Pharmacology (12.3)].

Patients with cGVHD

Avoid use of IMBRUVICA in patients with total bilirubin level > 3 x ULN (unless of non-hepatic origin or due to Gilbert’s syndrome). Reduce recommended dose when administering IMBRUVICA to patients with total bilirubin level > 1.5 to 3 x ULN (unless of non-hepatic origin or due to Gilbert’s syndrome) [see Dosage and Administration (2.4)].

8.7 Plasmapheresis

Management of hyperviscosity in WM patients may include plasmapheresis before and during treatment with IMBRUVICA. Modifications to IMBRUVICA dosing are not required.

10 OVERDOSAGE

There is no specific experience in the management of ibrutinib overdose in patients. One healthy subject experienced reversible Grade 4 hepatic enzyme increases (AST and ALT) after a dose of 1680 mg. Closely monitor patients who ingest more than the recommended dosage and provide appropriate supportive treatment.

11 DESCRIPTION

Ibrutinib is a kinase inhibitor. It is a white to off-white solid with the empirical formula C25H24N6O2 and a molecular weight 440.50. Ibrutinib is freely soluble in dimethyl sulfoxide, soluble in methanol and practically insoluble in water. The chemical name for ibrutinib is 1-[(3R)-3-[4-amino-3-(4-phenoxyphenyl)-1H-pyrazolo[3,4-d]pyrimidin-1-yl]-1-piperidinyl]-2-propen-1-one and has the following structure:

IMBRUVICA (ibrutinib) is available as immediate-release oral capsules, immediate-release oral tablets, and immediate-release oral suspension.

IMBRUVICA (ibrutinib) capsules for oral use are available in the following dosage strengths: 70 mg and 140 mg. Each capsule contains ibrutinib (active ingredient) and the following inactive ingredients: croscarmellose sodium, magnesium stearate, microcrystalline cellulose, sodium lauryl sulfate. The capsule shell contains gelatin, titanium dioxide, yellow iron oxide (70 mg capsule only), and black ink.

IMBRUVICA (ibrutinib) tablets for oral use are available in the following dosage strengths: 140 mg, 280 mg, and 420 mg. Each tablet contains ibrutinib (active ingredient) and the following inactive ingredients: colloidal silicon dioxide, croscarmellose sodium, lactose monohydrate, magnesium stearate, microcrystalline cellulose, povidone, and sodium lauryl sulfate. The film coating for each tablet contains ferrosoferric oxide (140 mg, 280 mg, and 420 mg tablets), polyvinyl alcohol, polyethylene glycol, red iron oxide (280 mg tablets), talc, titanium dioxide, and yellow iron oxide (140 mg and 420 mg tablets).

IMBRUVICA (ibrutinib) oral suspension contains 70 mg/mL ibrutinib (active ingredient) and the following inactive ingredients: benzyl alcohol, citric acid monohydrate, disodium hydrogen phosphate, hypromellose, microcrystalline cellulose and carboxymethylcellulose sodium, purified water and sucralose.

12 CLINICAL PHARMACOLOGY

12.1 Mechanism of Action

Ibrutinib is a small-molecule inhibitor of Bruton’s tyrosine kinase (BTK). Ibrutinib forms a covalent bond with a cysteine residue in the BTK active site, leading to inhibition of BTK enzymatic activity. BTK is a signaling molecule of the B-cell antigen receptor (BCR) and cytokine receptor pathways. BTK’s role in signaling through the B-cell surface receptors results in activation of pathways necessary for B-cell trafficking, chemotaxis, and adhesion. Nonclinical studies show that ibrutinib inhibits malignant B-cell proliferation and survival in vivo as well as cell migration and substrate adhesion in vitro.

12.2 Pharmacodynamics

In patients with recurrent B-cell lymphoma > 90% occupancy of the BTK active site in peripheral blood mononuclear cells was observed up to 24 hours after ibrutinib doses of ≥ 2.5 mg/kg/day (≥ 175 mg/day for average weight of 70 kg).

In adult patients with cGVHD, 93% occupancy of the BTK active site in peripheral blood mononuclear cells was observed at the ibrutinib recommended dose. The mean BTK occupancy in pediatric patients ranged from 95.1% to 99.6%.

In vitro Platelet Aggregation

Ibrutinib demonstrated inhibition of collagen-induced platelet aggregation, with IC50 values at 4.6 µM (2026 ng/mL), 0.8 µM (352 ng/mL), and 3 µM (1321 ng/mL) in blood samples from healthy donors, donors taking warfarin, and donors with severe renal dysfunction, respectively. Ibrutinib did not show meaningful inhibition of platelet aggregation for ADP, arachidonic acid, ristocetin, and TRAP-6.

Cardiac Electrophysiology

At a single dose 4 times the maximum recommended dose (1680 mg), IMBRUVICA did not prolong the QT interval to any clinically relevant extent.

12.3 Pharmacokinetics

Ibrutinib exposure increases with doses up to 840 mg (2 times the maximum approved recommended dosage) in patients with B-cell malignancies. The mean steady-state AUC (% coefficient of variation) observed in patients at 420 mg with CLL/SLL is 708 (71%) ng×h/mL, with WM is 707 (72%) ng×h/mL, and in adult patients with previously treated cGVHD is 1159 (50%) ng×h/mL. Steady-state concentrations of ibrutinib without CYP3A inhibitors were achieved with an accumulation ratio of 1 to 1.6 after 1 week of multiple daily doses of 420 mg.

Absorption

Absolute bioavailability of ibrutinib in fasted condition was 2.9% (90% CI: 2.1, 3.9) in healthy subjects. Ibrutinib is absorbed after oral administration with a median Tmax of 1 hour to 2 hours.

Effect of Food

The administration of IMBRUVICA with a high-fat and high-calorie meal (800 calories to 1,000 calories with approximately 50% of total caloric content of the meal from fat) increased ibrutinib Cmax by 2- to 4-fold and AUC by approximately 2-fold, compared with administration of ibrutinib after overnight fasting.

In vitro studies suggest that ibrutinib is not a substrate of p-glycoprotein (P-gp) or breast cancer resistance protein (BCRP).

Distribution

Reversible binding of ibrutinib to human plasma protein in vitro was 97.3% with no concentration dependence in the range of 50 ng/mL to 1000 ng/mL. The volume of distribution (Vd) was 683 L, and the apparent volume of distribution at steady state (Vd,ss/F) was approximately 10,000 L.

Elimination

Intravenous clearance was 62 L/h in fasted conditions and 76 L/h in fed conditions. In line with the high first-pass effect, the apparent oral clearance is 2000 L/h in fasted conditions and 1000 L/h in fed conditions. The half-life of ibrutinib is 4 hours to 6 hours.

Metabolism

Metabolism is the main route of elimination for ibrutinib. It is metabolized to several metabolites primarily by cytochrome P450 (CYP) 3A and to a minor extent by CYP2D6. The active metabolite, PCI-45227, is a dihydrodiol metabolite with inhibitory activity towards BTK approximately 15 times lower than that of ibrutinib. The range of the mean metabolite to parent ratio for PCI-45227 at steady-state is 1 to 2.8.

Excretion

Ibrutinib, mainly in the form of metabolites, is eliminated primarily via feces. After a single oral administration of radiolabeled ibrutinib, 90% of radioactivity was excreted within 168 hours, with 80% excreted in the feces and less than 10% eliminated in urine. Unchanged ibrutinib accounted for 1% of the radiolabeled excreted dose in feces and none in urine, with the remainder of the excreted dose being metabolites.

Specific Populations

Age and Sex

Age and sex have no clinically meaningful effect on ibrutinib pharmacokinetics.

Patients with Renal Impairment

Mild and moderate renal impairment (creatinine clearance [CLcr] > 25 mL/min as estimated by Cockcroft-Gault equation) had no influence on the exposure of ibrutinib. No data is available in patients with severe renal impairment (CLcr < 25 mL/min) or in patients on dialysis.

Patients with Hepatic Impairment

The AUC of ibrutinib increased 2.7-fold in subjects with mild hepatic impairment (Child-Pugh class A), 8.2-fold in subjects with moderate hepatic impairment (Child-Pugh class B) and 9.8-fold in subjects with severe hepatic impairment (Child-Pugh class C) relative to subjects with normal liver function. The Cmax of ibrutinib increased 5.2-fold in mild hepatic impairment, 8.8-fold in moderate hepatic impairment and 7-fold in severe hepatic impairment relative to subjects with normal liver function [see Use in Specific Populations (8.6)].

Pediatric Patients

In pediatric patients with cGVHD treated with ibrutinib at 240 mg/m^2 once daily (patients age ≥ 1 to < 12 years) or 420 mg once daily (patients age ≥ 12 years), the geometric mean (%CV) steady state AUC and Cmax in patients age ≥ 1 to < 12 years is 467 (102%) ng×h/mL and 65.7 (96%) ng/mL, respectively, and in patients age ≥ 12 to < 17 years is 966 (78%) ng×h/mL and 149 (79%) ng/mL, respectively.

Drug Interaction Studies

Clinical Studies and Model-Informed Approaches

Effect of CYP3A Inhibitors on Ibrutinib: The coadministration of multiple doses of ketoconazole (strong CYP3A inhibitor) increased the Cmax of ibrutinib by 29-fold and AUC by 24-fold. The coadministration of multiple doses of voriconazole (strong CYP3A inhibitor) increased steady state Cmax of ibrutinib by 6.7-fold and AUC by 5.7-fold. Simulations under fed conditions suggest that posaconazole (strong CYP3A inhibitor) may increase the AUC of ibrutinib 3-fold to 10-fold.

The coadministration of multiple doses of erythromycin (moderate CYP3A inhibitor) increased steady state Cmax of ibrutinib by 3.4-fold and AUC by 3-fold.

Effect of CYP3A Inducers on Ibrutinib: The coadministration of rifampin (strong CYP3A inducer) decreased the Cmax of ibrutinib by more than 13-fold and AUC by more than 10-fold. Simulations suggest that efavirenz (moderate CYP3A inducer) may decrease the AUC of ibrutinib by 3-fold.

In Vitro Studies

Effect of Ibrutinib on CYP Substrates: In vitro studies suggest that ibrutinib and PCI-45227 are unlikely to inhibit CYP1A2, 2B6, 2C8, 2C9, 2C19, 2D6 or 3A at clinical doses. Both ibrutinib and PCI-45227 are unlikely to induce CYP1A2, CYP2B6 or CYP3A at clinical doses.

Effect of Ibrutinib on Substrates of Transporters: In vitro studies suggest that ibrutinib may inhibit BCRP and P-gp transport at clinical doses. The coadministration of oral P-gp or BCRP substrates (e.g., digoxin, methotrexate) with IMBRUVICA may increase their concentrations.

13 NONCLINICAL TOXICOLOGY

13.1 Carcinogenesis, Mutagenesis, Impairment of Fertility

Ibrutinib was not carcinogenic in a 6-month rasH2 mouse study at oral doses up to 2000 mg/kg/day resulting in exposures approximately 32 (males) to 52 (females) times higher than the exposure in humans at a dose of 420 mg daily [see Warnings and Precautions (5.6)].

Ibrutinib was not mutagenic in a bacterial mutagenicity (Ames) assay, was not clastogenic in a chromosome aberration assay in mammalian (CHO) cells, nor was it clastogenic in an in vivo bone marrow micronucleus assay in mice at doses up to 2000 mg/kg.

Rats were administered oral daily doses of ibrutinib for 4 weeks prior to pairing and during pairing in males and 2 weeks prior to pairing and during pairing in females. Treatment of female rats continued following pregnancy up to gestation day (GD) 7, and treatment of male rats continued until end of study. No effects on fertility or reproductive capacities were observed in male or female rats up to the maximum dose tested, 100 mg/kg/day (Human Equivalent Dose [HED] 16 mg/kg).

14 CLINICAL STUDIES

14.1 Chronic Lymphocytic Leukemia / Small Lymphocytic Lymphoma

The safety and efficacy of IMBRUVICA in patients with CLL/SLL were demonstrated in one uncontrolled trial and five randomized, controlled trials.

Study 1102

Study 1102 (NCT01105247), an open-label, multi-center trial, was conducted in 48 previously treated CLL patients. IMBRUVICA was administered orally at 420 mg once daily until disease progression or unacceptable toxicity. The ORR and DOR were assessed using a modified version of the International Workshop on CLL Criteria by an Independent Review Committee.

The median age was 67 years (range, 37 to 82 years), 71% were male, and 94% were White. All patients had a baseline ECOG performance status of 0 or 1. The median time since diagnosis was 80 months and the median number of prior treatments was 4 (range, 1 to 12 treatments). At baseline, 46% of subjects had at least one tumor ≥ 5 cm.

The ORR was 58.3% (95% CI: 43.2%, 72.4%), all partial responses. None of the patients achieved a complete response. The DOR ranged from 5.6 to 24.2+ months. The median DOR was not reached.

RESONATE

The RESONATE study, a randomized, multicenter, open-label, phase 3 study of IMBRUVICA versus ofatumumab (NCT01578707), was conducted in patients with previously treated CLL or SLL. Patients (n=391) were randomized 1:1 to receive either IMBRUVICA 420 mg daily until disease progression, or unacceptable toxicity or ofatumumab at an initial dose of 300 mg, followed one week later by a dose of 2000 mg weekly for 7 doses and then every 4 weeks for 4 additional doses. Fifty-seven patients randomized to ofatumumab crossed over following progression to receive IMBRUVICA.

The median age was 67 years (range, 30 to 88 years), 68% were male, and 90% were White. All patients had a baseline ECOG performance status of 0 or 1. The trial enrolled 373 patients with CLL and 18 patients with SLL. The median time since diagnosis was 91 months and the median number of prior treatments was 2 (range, 1 to 13 treatments). At baseline, 58% of patients had at least one tumor ≥ 5 cm. Thirty-two percent of patients had 17p deletion.

Efficacy results for RESONATE are shown in Table 22 and the Kaplan-Meier curves for PFS, assessed by an IRC according to IWCLL criteria, and OS are shown in Figure 1 and Figure 2, respectively.

Table 22: Efficacy Results in Patients with CLL/SLL in RESONATE
Endpoint | IMBRUVICA N=195 | Ofatumumab N=196
Progression-Free Survivalb
Number of events (%) | 35 (17.9) | 111 (56.6)
Disease progression | 26 | 93
Death events | 9 | 18
Median (95% CI), months | NE | 8.1 (7.2, 8.3)
HR (95% CI) | 0.22 (0.15, 0.32)
Overall Survivala
Number of deaths (%) | 16 (8.2) | 33 (16.8)
HR (95% CI) | 0.43 (0.24, 0.79)
Overall Response Rateb | 42.6% | 4.1%

a Median OS not evaluable for either arm.

b IRC evaluated. All partial responses achieved; none of the patients achieved a complete response.

CI = confidence interval; HR = hazard ratio; NE = not evaluable.

Figure 1: Kaplan-Meier Curve of Progression-Free Survival (ITT Population) in Patients with CLL/SLL in RESONATE

Figure 2: Kaplan-Meier Curve of Overall Survival (ITT Population) in Patients with CLL/SLL in RESONATE

63-Month Follow-Up

With an overall follow-up of 63 months, the median investigator-assessed PFS per IWCLL criteria was 44.1 months [95% CI (38.5, 56.9)] in the IMBRUVICA arm and 8.1 months [95% CI (7.8, 8.3)] in the ofatumumab arm. Overall response rate as assessed by investigators was 87.2% in the IMBRUVICA arm versus 22.4% in the ofatumumab arm.

CLL/SLL with 17p deletion (del 17p CLL/SLL) in RESONATE

RESONATE included 127 patients with del 17p CLL/SLL. The median age was 67 years (range, 30 to 84 years), 62% were male, and 88% were White. All patients had a baseline ECOG performance status of 0 or 1. PFS and ORR were assessed by an IRC. Efficacy results for del 17p CLL/SLL are shown in Table 23.

Table 23: Efficacy Results in Patients with del 17p CLL/SLL in RESONATE
Endpoint | IMBRUVICA N=63 | Ofatumumab N=64
Progression-Free Survivala
Number of events (%) | 16 (25.4) | 38 (59.4)
Disease progression | 12 | 31
Death events | 4 | 7
Median (95% CI), months | NE | 5.8 (5.3, 7.9)
HR (95% CI) | 0.25 (0.14, 0.45)
Overall Response Ratea | 47.6% | 4.7%

a IRC evaluated. All partial responses achieved; none of the patients achieved a complete response.

CI = confidence interval; HR = hazard ratio; NE = not evaluable.

63-Month Follow-Up

With an overall follow-up of 63 months, the median investigator-assessed PFS in patients with del 17p per IWCLL criteria was 40.6 months [95% CI (25.4, 44.6)] in the IMBRUVICA arm and 6.2 months [95% CI (4.6, 8.1)] in the ofatumumab arm. Overall response rate as assessed by investigators in patients with del 17p was 88.9% in the IMBRUVICA arm versus 18.8% in the ofatumumab arm.

RESONATE-2

The RESONATE-2 study, a randomized, multicenter, open-label, phase 3 study of IMBRUVICA versus chlorambucil (NCT01722487), was conducted in patients with treatment naïve CLL or SLL who were 65 years of age or older. Patients (n = 269) were randomized 1:1 to receive either IMBRUVICA 420 mg daily until disease progression or unacceptable toxicity, or chlorambucil at a starting dose of 0.5 mg/kg on Days 1 and 15 of each 28-day cycle for a maximum of 12 cycles, with an allowance for intrapatient dose increases up to 0.8 mg/kg based on tolerability.

The median age was 73 years (range, 65 to 90 years), 63% were male, and 91% were White. Ninety one percent of patients had a baseline ECOG performance status of 0 or 1 and 9% had an ECOG performance status of 2. The trial enrolled 249 patients with CLL and 20 patients with SLL. At baseline, 20% of patients had 11q deletion. The most common reasons for initiating CLL therapy include: progressive marrow failure demonstrated by anemia and/or thrombocytopenia (38%), progressive or symptomatic lymphadenopathy (37%), progressive or symptomatic splenomegaly (30%), fatigue (27%) and night sweats (25%).

With a median follow-up of 28.1 months, there were 32 observed death events [11 (8.1%) and 21 (15.8%) in IMBRUVICA and chlorambucil treatment arms, respectively]. With 41% of patients switching from chlorambucil to IMBRUVICA, the overall survival analysis in the ITT patient population resulted in a statistically significant HR of 0.44 [95% CI (0.21, 0.92)] and 2-year survival rate estimates of 94.7% [95% CI (89.1, 97.4)] and 84.3% [95% CI (76.7, 89.6)] in the IMBRUVICA and chlorambucil arms, respectively.

Efficacy results for RESONATE-2 are shown in Table 24 and the Kaplan-Meier curve for PFS, assessed by an IRC according to IWCLL criteria is shown in Figure 3.

Table 24: Efficacy Results in Patients with CLL/SLL in RESONATE-2
Endpoint | IMBRUVICA N=136 | Chlorambucil N=133
Progression-Free Survivala
Number of events (%) | 15 (11.0) | 64 (48.1)
Disease progression | 12 | 57
Death events | 3 | 7
Median (95% CI), months | NE | 18.9 (14.1, 22.0)
HRb (95% CI) | 0.16 (0.09, 0.28)
Overall Response Ratea (CR + PR) | 82.4% | 35.3%
P-value | <0.0001

a IRC evaluated; five subjects (3.7%) in the IMBRUVICA arm and two subjects (1.5%) in the Chlorambucil arm achieved complete response.

b HR = hazard ratio; NE = not evaluable.

Figure 3: Kaplan-Meier Curve of Progression-Free Survival (ITT Population) in Patients with CLL/SLL in RESONATE-2

55-Month Follow-Up

With an overall follow-up of 55 months, the median PFS was not reached in the IMBRUVICA arm.

HELIOS

The HELIOS study, a randomized, double-blind, placebo-controlled phase 3 study of IMBRUVICA in combination with bendamustine and rituximab (BR) (NCT01611090), was conducted in patients with previously treated CLL or SLL. Patients (n = 578) were randomized 1:1 to receive either IMBRUVICA 420 mg daily or placebo in combination with BR until disease progression, or unacceptable toxicity. All patients received BR for a maximum of six 28-day cycles. Bendamustine was dosed at 70 mg/m^2 infused IV over 30 minutes on Cycle 1, Days 2 and 3, and on Cycles 2-6, Days 1 and 2 for up to 6 cycles, and all patients had a CLcr ≥ 40 mL/min at baseline. Rituximab was administered at a dose of 375 mg/m^2 in the first cycle, Day 1, and 500 mg/m^2 Cycles 2 through 6, Day 1.

The median age was 64 years (range, 31 to 86 years), 66% were male, and 91% were White. All patients had a baseline ECOG performance status of 0 or 1. The median time since diagnosis was 5.9 years and the median number of prior treatments was 2 (range, 1 to 11 treatments). At baseline, 56% of patients had at least one tumor > 5 cm and 26% presented with del11q.

Efficacy results for HELIOS are shown in Table 25 and the Kaplan-Meier curves for PFS are shown in Figure 4.

Table 25: Efficacy Results in Patients with CLL/SLL in HELIOS
Endpoint | IMBRUVICA + BR N=289 | Placebo + BR N=289
Progression-Free Survivala
Number of events (%) | 56 (19.4) | 183 (63.3)
Median (95% CI), months | NE | 13.3 (11.3, 13.9)
HR (95% CI) | 0.20 (0.15, 0.28)
Overall Response Ratea | 82.7% | 67.8%

a IRC evaluated; twenty-four subjects (8.3%) in the IMBRUVICA + BR arm and six subjects (2.1%) in the placebo + BR arm achieved complete response.

BR = bendamustine and rituximab; CI = confidence interval; HR = hazard ratio; NE = not evaluable.

Figure 4: Kaplan-Meier Curve of Progression-Free Survival (ITT Population) in Patients with CLL/SLL in HELIOS

iLLUMINATE

The iLLUMINATE study, a randomized, multi-center, phase 3 study of IMBRUVICA in combination with obinutuzumab versus chlorambucil in combination with obinutuzumab (NCT02264574), was conducted in patients with treatment naïve CLL or SLL. Patients were 65 years of age or older or < 65 years of age with coexisting medical conditions, reduced renal function as measured by creatinine clearance < 70 mL/min, or presence of del 17p/TP53 mutation. Patients (n = 229) were randomized 1:1 to receive either IMBRUVICA 420 mg daily until disease progression or unacceptable toxicity or chlorambucil at a dose of 0.5 mg/kg on Days 1 and 15 of each 28-day cycle for 6 cycles. In both arms, patients received 1,000 mg of obinutuzumab on Days 1, 8, and 15 of the first cycle, followed by treatment on the first day of 5 subsequent cycles (total of 6 cycles, 28 days each). The first dose of obinutuzumab was divided between Day 1 (100 mg) and Day 2 (900 mg).

The median age was 71 years (range, 40 to 87 years), 64% were male, and 96% were White. All patients had a baseline ECOG performance status of 0 (48%) or 1-2 (52%). The trial enrolled 214 patients with CLL and 15 patients with SLL. At baseline, 65% of patients presented with CLL/SLL with high risk factors (del 17p/TP53 mutation [18%], del 11q [15%], or unmutated immunoglobulin heavy-chain variable region (unmutated IGHV) [54%]). The most common reasons for initiating CLL therapy included: lymphadenopathy (38%), night sweats (34%), progressive marrow failure (31%), fatigue (29%), splenomegaly (25%), and progressive lymphocytosis (21%).

With a median follow-up time on study of 31 months, efficacy results for iLLUMINATE assessed by an IRC according to IWCLL criteria are shown in Table 26, and the Kaplan-Meier curve for PFS is shown in Figure 5.

Table 26: Efficacy Results in Patients with CLL/SLL in iLLUMINATE
Endpoint | IMBRUVICA + Obinutuzumab N=113 | Chlorambucil + Obinutuzumab N=116
Progression-Free Survivala
Number of events (%) | 24 (21) | 74 (64)
Disease progression | 11 | 64
Death events | 13 | 10
Median (95% CI), months | NE | 19.0 (15.1, 22.1)
HR (95% CI) | 0.23 (0.15, 0.37)
P-valueb | <0.0001
Overall Response Rate (%) a | 88.5 | 73.3
CRc (%) | 19.5 | 7.8
PRd (%) | 69.0 | 65.5

a IRC-evaluated.

b P-value is from unstratified log-rank test.

c Includes 1 patient in the IMBRUVICA + obinutuzumab arm with a complete response with incomplete marrow recovery (CRi)

d PR = nPR +PR.

HR = hazard ratio; NE = not evaluable.

Figure 5: Kaplan-Meier Curve of Progression-Free Survival (ITT Population) in Patients with CLL/SLL in iLLUMINATE

In the high risk CLL/SLL population (del 17p/TP53 mutation, del 11q, or unmutated IGHV), the PFS HR was 0.15 [95% CI (0.09, 0.27)].

E1912

The E1912 study, a randomized, multi-center, phase 3 study of IMBRUVICA in combination with rituximab versus standard fludarabine, cyclophosphamide, and rituximab (FCR) chemoimmunotherapy (NCT02048813), was conducted in adult patients who were 70 years or younger with previously untreated CLL or SLL requiring systemic therapy. All patients had a CLcr > 40 mL/min at baseline. Patients with 17p deletion were excluded. Patients (n =529) were randomized 2:1 to receive either IMBRUVICA plus rituximab or FCR. IMBRUVICA was administered at 420 mg daily until disease progression or unacceptable toxicity. Fludarabine was administered at a dose of 25 mg/m^2, and cyclophosphamide was administered at a dose of 250 mg/m^2, both on Days 1, 2, and 3 of Cycles 1-6. Rituximab was initiated in Cycle 2 for the IMBRUVICA plus rituximab arm and in Cycle 1 for the FCR arm and was administered at 50 mg/m^2 on Day 1 of the first cycle, 325 mg/m^2 on Day 2 of the first cycle, and 500 mg/m^2 on Day 1 of 5 subsequent cycles, for a total of 6 cycles. Each cycle was 28 days.

The median age was 58 years (range, 28 to 70 years), 67% were male, 90% were White and 98% had a ECOG performance status of 0-1. At baseline, 43% of patients were Rai stage 3 or 4 and 59% of patients presented with high risk factors (TP53 mutation [6%], del11q [22%], or unmutated IGHV [53%]).

With a median follow-up time on study of 37 months, efficacy results for E1912 are shown in Table 27. The Kaplan-Meier curves for PFS, assessed according to IWCLL criteria is shown in Figure 6.

Table 27: Efficacy Results in Patients with CLL/SLL in E1912
Endpoint | IMBRUVICA + R N=354 | FCR N=175
Progression-Free Survival
Number of events (%) | 41 (12) | 44 (25)
Disease progression | 39 | 38
Death events | 2 | 6
Median (95% CI), months | NE (49.4, NE) | NE (47.1, NE)
HR (95% CI) | 0.34 (0.22, 0.52)
P-valuea | <0.0001

a P-value is from unstratified log-rank test.

FCR = fludarabine, cyclophosphamide, and rituximab; HR = hazard ratio; R = rituximab; NE = not evaluable.

Figure 6: Kaplan-Meier Curve of Progression-Free Survival (ITT Population) in Patients with CLL/SLL in E1912

With a median follow-up time on study of 49 months, median overall survival was not reached with a total of 23 deaths: 11 (3%) in the IMBRUVICA plus rituximab and 12 (7%) in the FCR treatment arms.

Lymphocytosis

Upon initiation of single-agent IMBRUVICA, an increase in lymphocyte counts (i.e., ≥ 50% increase from baseline and above absolute lymphocyte count of 5,000/mcL) occurred in 66% of patients in the CLL studies. The onset of isolated lymphocytosis occurs during the first month of IMBRUVICA therapy and resolves by a median of 14 weeks (range, 0.1 to 104 weeks). When IMBRUVICA was administered in combination, lymphocytosis was 7% with IMBRUVICA + BR versus 6% with placebo + BR and 7% with IMBRUVICA + obinutuzumab versus 1% with chlorambucil + obinutuzumab.

14.2 Waldenström’s Macroglobulinemia

The safety and efficacy of IMBRUVICA in patients with WM were demonstrated in two single-arm trials and one randomized, controlled trial.

Study 1118 and INNOVATE Monotherapy Arm

Study 1118 (NCT01614821), an open-label, multi-center, single-arm trial was conducted in 63 previously treated patients with WM. IMBRUVICA was administered orally at 420 mg once daily until disease progression or unacceptable toxicity. The responses were assessed by investigators and an IRC using criteria adopted from the International Workshop of Waldenström’s Macroglobulinemia.

The median age was 63 years (range, 44 to 86 years), 76% were male, and 95% were White. All patients had a baseline ECOG performance status of 0 or 1. The median time since diagnosis was 74 months, and the median number of prior treatments was 2 (range, 1 to 11 treatments). At baseline, the median serum IgM value was 3.5 g/dL (range, 0.7 to 8.4 g/dL).

Responses, defined as partial response or better, per IRC are shown in Table 28.

Table 28: Response Rate and Duration of Response (DOR) Based on IRC Assessment in Patients with WM in Study 1118
 | Total (N=63)
Response rate (CR+VGPR+PR), (%) | 61.9
95% CI (%) | (48.8, 73.9)
Complete Response (CR) | 0
Very Good Partial Response (VGPR), (%) | 11.1
Partial Response (PR), (%) | 50.8
Median duration of response, months (range) | NE (2.8+, 18.8+)
CI = confidence interval; NE = not evaluable.

The median time to response was 1.2 months (range, 0.7-13.4 months).

The INNOVATE monotherapy arm included 31 patients with previously treated WM who failed prior rituximab-containing therapy and received single-agent IMBRUVICA. The median age was 67 years (range, 47 to 90 years). Eighty-one percent of patients had a baseline ECOG performance status of 0 or 1, and 19% had a baseline ECOG performance status of 2. The median number of prior treatments was 4 (range, 1 to 7 treatments). With an overall follow-up of 61 months, the response rate observed in the INNOVATE monotherapy arm per IRC assessment was 77% (0% CR, 29% VGPR, 48% PR). The median duration of response was 33 months (range, 2.4 to 60.2+ months).

INNOVATE

The INNOVATE study, a randomized, double-blind, placebo-controlled, phase 3 study of IMBRUVICA or placebo in combination with rituximab (NCT02165397), was conducted in treatment naïve or previously treated patients with WM. Patients (n = 150) were randomized 1:1 to receive either IMBRUVICA 420 mg daily or placebo in combination with rituximab until disease progression or unacceptable toxicity. Rituximab was administered weekly at a dose of 375 mg/m^2 for 4 consecutive weeks (weeks 1-4) followed by a second course of weekly rituximab for 4 consecutive weeks (weeks 17-20). The major efficacy outcome measure is progression-free survival (PFS) assessed by an IRC with additional efficacy measure of response rate.

The median age was 69 years (range, 36 to 89 years), 66% were male, and 79% were White. Ninety-three percent of patients had a baseline ECOG performance status of 0 or 1, and 7% of patients had a baseline ECOG performance status of 2. Forty-five percent of patients were treatment naïve, and 55% of patients were previously treated. Among previously treated patients, the median number of prior treatments was 2 (range, 1 to 6 treatments). At baseline, the median serum IgM value was 3.2 g/dL (range, 0.6 to 8.3 g/dL), and MYD88 L265P mutations were present in 77% of patients, absent in 13% of patients, and 9% of patients were not evaluable for mutation status.

An exploratory analysis demonstrated a sustained hemoglobin improvement (defined as increase of ≥ 2 g/dL over baseline for at least 8 weeks without blood transfusions or growth factor support) in 65% of patients in the IMBRUVICA + R group and 39% of patients in the placebo + R group.

With an overall follow-up of 63 months, efficacy results as assessed by an IRC at the time of the final analysis for INNOVATE are shown in Table 29, and the Kaplan-Meier curves for PFS are shown in Figure 7.

Table 29: Efficacy Results in Patients with WM by IRC in INNOVATE (Final Analysis)
Endpoint | IMBRUVICA + R N=75 | Placebo + R N=75
Progression-Free Survival
Number of events (%) | 22 (29) | 50 (67)
Median (95% CI), months | NE (57.7, NE) | 20.3 (13.0, 27.6)
HR (95% CI) | 0.25 (0.15, 0.42)
P-valuea | <0.0001
Response Rate (CR+VGPR+PR) b | 76% | 31%
95% CI (%) | (65, 85) | (21, 42)
Complete Response (CR) | 1% | 1%
Very Good Partial Response (VGPR) | 29% | 4%
Partial Response (PR) | 45% | 25%
Median duration of response, months (range) | NE (1.9+, 58.9+) | NE (4.6+, 49.7+)

CI = confidence interval; HR = hazard ratio; NE = not evaluable; R = rituximab.

a P-value is from the stratified log-rank test.

b P-value associated with response rate was <0.0001.

Figure 7: Kaplan-Meier Curve of Progression-Free Survival (ITT Population) in Patients with WM in INNOVATE

Median overall survival was not reached for either treatment arm. With an overall follow-up of 63 months, 9 (12%) patients on IMBRUVICA + R and 10 (13.3%) patients on placebo + R had died. Forty-seven percent of patients randomized to the placebo + R arm crossed over to receive IMBRUVICA.

14.3 Chronic Graft versus Host Disease

Study 1129

The safety and efficacy of IMBRUVICA in cGVHD were evaluated in Study 1129 (NCT02195869), an open-label, multi-center, single-arm trial of 42 patients with cGVHD after failure of first line corticosteroid therapy and requiring additional therapy. IMBRUVICA was administered orally at 420 mg once daily. The responses were assessed by investigators using the 2005 National Institute of Health (NIH) Consensus Panel Response Criteria with two modifications to align with the updated 2014 NIH Consensus Panel Response Criteria.

The median age was 56 years (range, 19 to 74 years), 52% were male, and 93% were White. The most common underlying malignancies leading to transplantation were acute lymphocytic leukemia, acute myeloid leukemia, and CLL. The median time since cGVHD diagnosis was 14 months, the median number of prior cGVHD treatments was 2 (range, 1 to 3 treatments), and 60% of patients had a Karnofsky performance score of ≤ 80. The majority of patients (88 %) had at least 2 organs involved at baseline, with the most commonly involved organs being mouth (86%), skin (81%), and gastrointestinal tract (33%). The median daily corticosteroid dose (prednisone or prednisone equivalent) at baseline was 0.3 mg/kg/day, and 52% of patients were receiving ongoing immunosuppressants in addition to systemic corticosteroids at baseline. Prophylaxis for infections were managed per institutional guidelines with 79% of patients receiving combinations of sulfonamides and trimethoprim and 64% receiving triazole derivatives.

Efficacy results are shown in Table 30.

Table 30: Best Overall Response Rate (ORR) and Sustained Response Rate Based on Investigator Assessmenta in Patients with cGVHD in Study 1129
 | Total (N=42)
ORR | 28 (67%)
95% CI | (51%, 80%)
Complete Response (CR) | 9 (21%)
Partial Response (PR) | 19 (45%)
Sustained response rateb | 20 (48%)
CI = confidence interval.
a Investigator assessment based on the 2005 NIH Response Criteria with two modifications (added “not evaluable” for organs with non-cGVHD abnormalities, and organ score change from 0 to 1 was not considered disease progression.)
b Sustained response rate is defined as the proportion of patients who achieved a CR or PR that was sustained for at least 20 weeks.

The median time to response coinciding with the first scheduled response assessment was 12.3 weeks (range, 4.1 to 42.1 weeks). Responses were seen across all organs involved for cGVHD (skin, mouth, gastrointestinal tract, and liver).

ORR results were supported by exploratory analyses of patient-reported symptom bother which showed at least a 7-point decrease in Lee Symptom Scale overall summary score in 24% (10/42) of patients on at least 2 consecutive visits.

iMAGINE

The safety and efficacy of IMBRUVICA were evaluated in iMAGINE (NCT03790332), an open-label, multi-center, single-arm trial of IMBRUVICA for the treatment of pediatric and young adult patients age 1 year to less than 22 years with moderate or severe cGVHD as defined by NIH Consensus Criteria. The study included 47 patients who required additional therapy after failure of one or more prior lines of systemic therapy. All patients had platelets ≥ 30 x 10^9/L; absolute neutrophil count ≥ 1.0 x 10^9/L; AST or ALT ≤ 3 x ULN; total bilirubin of ≤ 1.5 x ULN; and estimated creatinine clearance ≥ 30 mL/min. Patients were excluded if single organ genitourinary involvement was the only manifestation of cGVHD.

Patients age 12 years and older were treated with IMBRUVICA 420 mg orally once daily, and patients age 1 year to less than 12 years were treated with IMBRUVICA 240 mg/m^2 orally once daily. Concomitant treatment with supportive care therapies for cGVHD was permitted. Initiation of new systemic cGVHD therapy while on study was not permitted.

The median age was 13 years (range, 1 to 19 years). Of the 47 patients, 70% of patients were male, and 36% were White, 9% were Black or African American, 55% were other or unreported. The median time since cGVHD diagnosis was 16.1 months, the median number of prior cGVHD treatments was 2 (range, 1 to 12). The majority of patients (87%) had at least 2 organs involved at baseline, with lung involvement at baseline in 49% of patients; 26% of patients had a Karnofsky/Lansky performance score of <80. The median daily corticosteroid dose (prednisone or prednisone equivalent) at baseline was 0.47 mg/kg/day, and 61% (19 of 31) patients were receiving ongoing immunosuppressants in addition to systemic corticosteroids at baseline. Prophylaxis for infections was managed per institutional guidelines, with 72% of patients receiving combinations of sulfonamides and trimethoprim and 70% receiving systemic antifungal agents.

The efficacy of IMBRUVICA was established based on overall response rate (ORR) through Week 25, where overall response included complete response or partial response according to the 2014 National Institutes of Health (NIH) Consensus Development Project Response Criteria. The efficacy results are shown in Table 31.

Table 31: Efficacy Results in Patients with Previously Treated cGVHDa in iMAGINE
 | Total (N=47)
ORR by Week 25 | 28 (60%)
95% CI (%) | (44, 74)
Complete Response (CR) | 2 (4%)
Partial Response (PR) | 26 (55%)
Median duration of response, months (95% CI) b | 5.3 (2.8, 8.8)

CI = confidence interval; ORR = overall response rate.

a Assessment based on 2014 NIH Consensus Development Project Response Criteria.

b Based on all responders in the study, calculated from first response to progression, death, or new systemic therapies for cGVHD.

The median time to first response was 0.9 month (range, 0.9 to 6.1 months). The median time from first response to death or new systemic therapies for cGVHD was 14.8 months (95% CI: 4.6, not evaluable).

ORR results were supported by exploratory analyses of patient-reported symptom bother which showed at least a 7-point decrease in Lee Symptom Scale overall summary score through Week 25 in 50% (13/26) of patients age 12 years and older.

16 HOW SUPPLIED/STORAGE AND HANDLING

Capsules

The 70 mg capsules are supplied as yellow opaque capsules, marked with “ibr 70 mg” in black ink, in white HDPE bottles with a child-resistant closure:

- 28 capsules per bottle: NDC 57962-070-28

The 140 mg capsules are supplied as white opaque capsules, marked with “ibr 140 mg” in black ink, in white HDPE bottles with a child-resistant closure:

- 90 capsules per bottle: NDC 57962-140-09
- 120 capsules per bottle: NDC 57962-140-12

Store bottles at room temperature 20°C to 25°C (68°F to 77°F). Brief exposure to 15°C to 30°C (59°F to 86°F) permitted (see USP Controlled Room Temperature). Retain in original package until dispensing.

Tablets

The IMBRUVICA (ibrutinib) tablets are supplied in 3 strengths in the following packaging configurations:

- 140 mg tablets: Yellow green to green round tablets debossed with “ibr” on one side and “140” on the other side. Carton of one folded blister card containing two 14-count blister strips for a total of 28 tablets: NDC 57962-014-28
- 280 mg tablets: Purple oblong tablets debossed with “ibr” on one side and “280” on the other side. Carton of one folded blister card containing two 14-count blister strips for a total of 28 tablets: NDC 57962-280-28
- 420 mg tablets: Yellow green to green oblong tablets debossed with “ibr” on one side and “420” on the other side. Carton of one folded blister card containing two 14-count blister strips for a total of 28 tablets: NDC 57962-420-28

Store tablets in original packaging at room temperature 20°C to 25°C (68°F to 77°F). Brief exposure to 15°C to 30°C (59°F to 86°F) permitted (see USP Controlled Room Temperature).

Oral Suspension

The IMBRUVICA (ibrutinib) oral suspension is a white to off-white suspension supplied as 108 mL in a 150 mL amber glass bottle with a pre-inserted bottle adapter and a child-resistant closure. Each mL contains 70 mg of ibrutinib. The oral suspension bottle is provided in a carton with two 3 mL reusable oral dosing syringes: NDC 57962-007-12.

Store the oral suspension bottle at 2°C to 25°C (36°F to 77°F). Do not freeze. Dispense in original sealed container. Do not use if the carton seal is broken or missing.

Discard any unused IMBRUVICA oral suspension remaining 60 days after first opening the bottle.

17 PATIENT COUNSELING INFORMATION

Advise the patients and caregivers to read the FDA-approved patient labeling (Patient Information and Instructions for Use).

Hemorrhage:
Inform patients of the possibility of bleeding, and to report any signs or symptoms (severe headache, blood in stools or urine, prolonged or uncontrolled bleeding). Inform the patient that IMBRUVICA may need to be interrupted for medical or dental procedures [see Warnings and Precautions (5.1)].

Infections:
Inform patients of the possibility of serious infection, and to report any signs or symptoms (fever, chills, weakness, confusion) suggestive of infection [see Warnings and Precautions (5.2)].

Cardiac arrhythmias, cardiac failure, and sudden death:

Inform patients of the possibility of irregular heart rhythm, heart failure and sudden death.
Counsel patients to report any signs of palpitations, lightheadedness, dizziness, fainting, shortness of breath, chest discomfort, or edema [see Warnings and Precautions (5.3)].

Hypertension:
Inform patients that high blood pressure has occurred in patients taking IMBRUVICA, which may require treatment with anti-hypertensive therapy [see Warnings and Precautions (5.4)].

Second primary malignancies:
Inform patients that other malignancies have occurred in patients who have been treated with IMBRUVICA, including skin cancers and other carcinomas [see Warnings and Precautions (5.6)].

Hepatotoxicity, including drug-induced liver injury:

Inform patients that liver problems, including drug-induced liver injury and abnormalities in liver tests, may develop during IMBRUVICA treatment. Advise patients to contact their healthcare provider immediately if they experience abdominal discomfort, dark urine, or jaundice [see Warnings and Precautions (5.7)].

Tumor lysis syndrome:
Inform patients of the potential risk of tumor lysis syndrome and to report any signs and symptoms associated with this event to their healthcare provider for evaluation [see Warnings and Precautions (5.8)].

Embryo-fetal toxicity:
Advise women of the potential risk to a fetus. Advise females of reproductive potential to inform their healthcare provider of a known or suspected pregnancy [see Warnings and Precautions (5.9), Use in Specific Populations (8.1)].
Advise females of reproductive potential to use effective contraception during treatment with IMBRUVICA and for 1 month after the last dose [see Use in Specific Populations (8.3)].
Advise males with female partners of reproductive potential to use effective contraception during treatment with IMBRUVICA and for 1 month after the last dose [see Use in Specific Populations (8.3), Nonclinical Toxicology (13.1)].

Lactation:
Advise women not to breastfeed during treatment with IMBRUVICA and for 1 week after the last dose [see Use in Specific Populations (8.2)].

Other Important Information:

Inform patients to take IMBRUVICA orally once daily according to their physician’s instructions and that the oral dosage (capsules or tablets) should be swallowed whole with a glass of water without opening, breaking or chewing the capsules or cutting, crushing or chewing the tablets approximately the same time each day [see Dosage and Administration (2.1)].

Advise patients that in the event of a missed daily dose of IMBRUVICA, it should be taken as soon as possible on the same day with a return to the normal schedule the following day. Patients should not take extra doses to make up the missed dose [see Dosage and Administration (2.1)].

For IMBRUVICA oral suspension, instruct patients or caregivers to read and follow the Instructions for Use for proper preparation, administration, storage and disposal [see Dosage and Administration (2.1)].

Advise patients of the common side effects associated with IMBRUVICA [see Adverse Reactions (6)]. Direct the patient to a complete list of adverse drug reactions in PATIENT INFORMATION.

Advise patients to inform their health care providers of all concomitant medications, including prescription medicines, over-the-counter drugs, vitamins, and herbal products [see Drug Interactions (7)].

Advise patients that they may experience loose stools or diarrhea and should contact their doctor if their diarrhea persists. Advise patients to maintain adequate hydration [see Adverse Reactions (6.1)].

Distributed and Marketed by:
Pharmacyclics LLC
South San Francisco, CA 94080 USA
and
Marketed by:
Janssen Biotech, Inc.
Horsham, PA 19044 USA

Patent http://www.imbruvica.com
IMBRUVICA® and its design are trademarks of Pharmacyclics, LLC, an AbbVie company.

© 2025 Pharmacyclics LLC. All rights reserved.

© 2025 Janssen Biotech, Inc. All rights reserved.

20096654

PATIENT INFORMATION

IMBRUVICA (im-BRU-vih-kuh)
(ibrutinib)
capsules

IMBRUVICA (im-BRU-vih-kuh)
(ibrutinib)
tablets

IMBRUVICA (im-BRU-vih-kuh)
(ibrutinib)
oral suspension

What is IMBRUVICA?
IMBRUVICA is a prescription medicine used to treat:

- Adults with chronic lymphocytic leukemia (CLL)/Small lymphocytic lymphoma (SLL).
- Adults with chronic lymphocytic leukemia (CLL)/Small lymphocytic lymphoma (SLL) with 17p deletion.
- Adults with Waldenström’s macroglobulinemia (WM).
- Adults and children 1 year of age and older with chronic graft versus host disease (cGVHD) after failure of 1 or more lines of systemic therapy.

It is not known if IMBRUVICA is safe and effective in children under 1 year of age.

Before taking IMBRUVICA, tell your healthcare provider about all of your medical conditions, including if you:

- have had recent surgery or plan to have surgery. Your healthcare provider may stop IMBRUVICA for any planned medical, surgical, or dental procedure.
- have bleeding problems or are taking a blood thinner medicine.
- have an infection.
- have or had heart rhythm problems, smoke, or have a medical condition that increases your risk of heart disease, such as high blood pressure, high cholesterol, or diabetes.
- have liver problems.
- are pregnant or plan to become pregnant. IMBRUVICA can harm your unborn baby. If you are able to become pregnant, your healthcare provider will do a pregnancy test before starting treatment with IMBRUVICA. Tell your healthcare provider if you are pregnant or think you may be pregnant during treatment with IMBRUVICA.
  ○ Females who are able to become pregnant should use effective birth control (contraception) during treatment with IMBRUVICA and for 1 month after the last dose.
  ○ Males with female partners who are able to become pregnant should use effective birth control, such as condoms, during treatment with IMBRUVICA and for 1 month after the last dose.
- are breastfeeding or plan to breastfeed. Do not breastfeed during treatment with IMBRUVICA and for 1 week after the last dose.

Tell your healthcare provider about all the medicines you take, including prescription and over-the-counter medicines, vitamins, and herbal supplements. Taking IMBRUVICA with certain other medicines may affect how IMBRUVICA works and can cause side effects.

How should I take or give IMBRUVICA?

- Take or give IMBRUVICA exactly as your healthcare provider tells you to take or give it.
- Take or give IMBRUVICA 1 time a day at about the same time each day.

IMBRUVICA comes as capsules, tablets, and oral suspension.

- If your healthcare provider prescribes IMBRUVICA capsules or tablets:
  ◦ Swallow IMBRUVICA capsules or tablets whole with a glass of water.
  ◦ Do not open, break, or chew IMBRUVICA capsules.
  ◦ Do not cut, crush, or chew IMBRUVICA tablets.
- If your healthcare provider prescribes IMBRUVICA oral suspension:
  ◦ See the detailed Instructions for Use that comes with IMBRUVICA oral suspension for information about the correct way to take or give a dose. If you have questions about how to take or give IMBRUVICA oral suspension, talk to your healthcare provider.
  ◦ Do not use if the carton seal is broken or missing.
- If you miss a dose of IMBRUVICA, take or give it as soon as you remember on the same day. Take or give the next dose of IMBRUVICA at the regular time on the next day. Do not take or give extra doses of IMBRUVICA to make up for a missed dose.
- If you take too much IMBRUVICA, call your healthcare provider, or go to the nearest hospital emergency room right away.

What should I avoid while taking IMBRUVICA?
You should not drink grapefruit juice, eat grapefruit, or eat Seville oranges (often used in marmalades) during treatment with IMBRUVICA. These products may increase the amount of IMBRUVICA in your blood.

What are the possible side effects of IMBRUVICA?
IMBRUVICA may cause serious side effects, including:

- Bleeding problems (hemorrhage) are common during treatment with IMBRUVICA and can also be serious and may lead to death. Your risk of bleeding may increase if you are also taking a blood thinner medicine. Tell your healthcare provider if you have any signs of bleeding, including:

- blood in your stools or black stools (looks like tar)
- pink or brown urine
- unexpected bleeding, or bleeding that is severe or that you cannot control
- vomit blood or vomit looks like coffee grounds
- cough up blood or blood clots

- increased bruising, or small red or purple spots on the skin
- dizziness
- weakness
- confusion
- change in your speech
- headache that lasts a long time or severe headache

- Infections can happen during treatment with IMBRUVICA. These infections can be serious and may lead to death. Tell your healthcare provider right away if you have fever, chills, weakness, confusion, or other signs or symptoms of an infection during treatment with IMBRUVICA.
- Heart problems. Serious heart rhythm problems (ventricular arrhythmias, atrial fibrillation, and atrial flutter), heart failure and death have happened in people treated with IMBRUVICA, especially in people who have an infection, an increased risk for heart disease, or have had heart rhythm problems in the past. Your heart function will be checked before and during treatment with IMBRUVICA. Tell your healthcare provider if you get any symptoms of heart problems, such as:

- feeling as if your heart is beating fast and irregular
- lightheadedness
- dizziness

- shortness of breath
- swelling of the feet, ankles, or legs

- chest discomfort
- feeling faint

If you develop any of these symptoms, your healthcare provider may do tests to check your heart and may change your IMBRUVICA dose.

- High blood pressure (hypertension). New or worsening high blood pressure has happened in people treated with IMBRUVICA. Your healthcare provider may start you on blood pressure medicine or change current medicines to treat your blood pressure.
- Decrease in blood cell counts. Decreased blood counts (white blood cells, platelets, and red blood cells) are common with IMBRUVICA, but can also be severe. Your healthcare provider should do monthly blood tests to check your blood counts.
- Second primary cancers. New cancers have happened during treatment with IMBRUVICA, including cancers of the skin or other organs.
- Liver problems. Liver problems, which may be severe or life-threatening, or lead to death, can happen in people treated with IMBRUVICA. Your healthcare provider will do blood tests to check your liver before and during treatment with IMBRUVICA. Tell your healthcare provider or get medical help right away if you have any signs of liver problems, including stomach pain or discomfort, dark-colored urine, or yellow skin and eyes.
- Tumor lysis syndrome (TLS). TLS is caused by the fast breakdown of cancer cells. TLS can cause kidney failure and the need for dialysis treatment, abnormal heart rhythm, seizure, and sometimes death. Your healthcare provider may do blood tests to check you for TLS.

The most common side effects of IMBRUVICA in adults with B-cell malignancies (CLL/SLL and WM) include:

- low platelet count

- muscle, bone, and joint pain

- low red blood cell count (anemia)

- diarrhea

- low white blood cell count

- bruising

- tiredness

- rash

- nausea

The most common side effects of IMBRUVICA in adults or children 1 year of age and older with cGVHD include:

- tiredness

- muscle, bone, and joint pain

- nausea

- low red blood cell count (anemia)

- fever

- stomach pain

- bruising

- muscle spasms

- pneumonia

- diarrhea

- mouth sores (stomatitis)

- headache

- low platelet count

- bleeding

Diarrhea is a common side effect in people who take IMBRUVICA. Drink plenty of fluids during treatment with IMBRUVICA to help reduce your risk of losing too much fluid (dehydration) due to diarrhea. Tell your healthcare provider if you have diarrhea that does not go away.
These are not all the possible side effects of IMBRUVICA.
Call your doctor for medical advice about side effects. You may report side effects to FDA at 1-800-FDA-1088.

How should I store IMBRUVICA?

- Store IMBRUVICA capsules and tablets at room temperature between 68°F and 77°F (20°C and 25°C).
- Keep IMBRUVICA capsules in the original container with the lid tightly closed.
- Keep IMBRUVICA tablets in the original carton.
- Store IMBRUVICA oral suspension bottle between 36°F and 77°F (2°C and 25°C). Do not freeze.
- Use IMBRUVICA oral suspension within 60 days after first opening the bottle. Throw away (dispose of) any unused portion 60 days after opening.
- IMBRUVICA capsules and oral suspension come in a bottle with a child-resistant cap.

Keep IMBRUVICA and all medicines out of the reach of children.

General information about the safe and effective use of IMBRUVICA.
Medicines are sometimes prescribed for purposes other than those listed in a Patient Information leaflet. Do not use IMBRUVICA for a condition for which it was not prescribed. Do not give IMBRUVICA to other people, even if they have the same symptoms that you have. It may harm them. You can ask your pharmacist or healthcare provider for information about IMBRUVICA that is written for health professionals.

What are the ingredients in IMBRUVICA?
Active ingredient: ibrutinib
Inactive ingredients:
IMBRUVICA capsules: croscarmellose sodium, magnesium stearate, microcrystalline cellulose, and sodium lauryl sulfate. The 70 mg capsule shell contains gelatin, titanium dioxide, yellow iron oxide, and black ink. The 140 mg capsule shell contains gelatin, titanium dioxide, and black ink.
IMBRUVICA tablets: colloidal silicon dioxide, croscarmellose sodium, lactose monohydrate, magnesium stearate, microcrystalline cellulose, povidone, and sodium lauryl sulfate. The film coating for each tablet contains ferrosoferric oxide (140 mg, 280 mg, and 420 mg tablets), polyvinyl alcohol, polyethylene glycol, red iron oxide (280 mg tablets), talc, titanium dioxide, and yellow iron oxide (140 mg and 420 mg tablets).
IMBRUVICA oral suspension: benzyl alcohol, citric acid monohydrate, disodium hydrogen phosphate, hypromellose, microcrystalline cellulose and carboxymethylcellulose sodium, purified water, and sucralose.
Distributed and Marketed by: Pharmacyclics LLC South San Francisco, CA 94080 USA
Marketed by: Janssen Biotech, Inc. Horsham, PA 19044 USA
© 2025 Pharmacyclics LLC. All rights reserved.
© 2025 Janssen Biotech, Inc. All rights reserved.
20096654
For more information, go to www.imbruvica.com or call 1-877-877-3536.

This Patient Information has been approved by the U.S. Food and Drug Administration. Revised: 10/2025

INSTRUCTIONS FOR USE

IMBRUVICA (im-BRU-vih-kuh)

(ibrutinib)

oral suspension

This Instructions for Use contains information about how to prepare and take or give a dose of IMBRUVICA oral suspension.

Read this Instructions for Use before you take or give IMBRUVICA and each time you get a refill. There may be new information.

This Instructions for Use does not take the place of talking to your healthcare provider about your or your child’s medical condition or treatment.

Call your healthcare provider or 1-877-877-3536 if you need help or have any questions about how to take or give IMBRUVICA the right way.

Important information you need to know before taking or giving IMBRUVICA.

- IMBRUVICA is for oral use only.
- Take or give IMBRUVICA exactly as your healthcare provider tells you to.
- If you miss a dose of IMBRUVICA, it can be taken or given as soon as possible on the same day. Do not take or give more than the prescribed dose in 1 day.

If you or your child take too much IMBRUVICA, call your healthcare provider for help.

- Keep these instructions for future use.

Each IMBRUVICA carton contains (see Figure A):

- 1 bottle of IMBRUVICA (called ‘bottle’ in this Instructions for Use) with pre-inserted bottle adapter (called ‘adapter’ in this Instructions for Use). Do not remove the bottle adapter.
- 2 reusable 3 mL oral dosing syringes (called ‘syringe’ in this Instructions for Use) measuring in 0.1 mL increments.

Only use the syringes that come with IMBRUVICA. Do not use the syringes for other patients or with other medicines.

If you cannot read the markings on the syringes, throw them away and call 1-877-877-3536 to get new ones.

Preparing and taking or giving a dose of IMBRUVICA

Step 1: Gather and check supplies.

- Check the prescribed dose in milliliters (mLs). Find this mL marking on the syringe.
- If the dose is more than the marking on the syringe, split the dose between syringes as prescribed.
- Gather bottle and syringe(s) (see Figure A).
- Check the bottle and make sure that the bottle has IMBRUVICA Oral Suspension printed on it and the expiration date (“EXP”) has not passed.

Figure A

Do not use IMBRUVICA after the “EXP” date printed on the carton and on the bottle.

Do not use if the IMBRUVICA carton seal appears to be tampered with.

Step 2: Record or check the discard date.

- When opening the bottle for the first time, record the date that is 60 days from the day the bottle is opened underneath the words “Discard Date” (see Figure B).
- Use IMBRUVICA within 60 days after first opening the bottle.

Figure B

Do not use IMBRUVICA past the discard date recorded on the bottle.

Step 3: Shake the bottle.

- Shake the bottle well before each use (see Figure C).

Figure C

Step 4: Remove the cap from the bottle.

- Press down and twist the cap counterclockwise to remove it from the bottle (see Figure D).
- If there is fluid on top of the adapter, you may wipe it with a clean disposable tissue.

Do not remove the bottle adapter.

Figure D

Step 5: Attach the syringe to the bottle.

- Make sure the syringe is clean and dry before use.
- Push the plunger down all the way.
- Gently insert tip of the syringe into the adapter.
- Turn the assembled bottle and syringe upside down (see Figure E).

Figure E

Step 6: Fill the syringe.

- Slowly pull the syringe plunger down, past the number of mLs for your prescribed dose (see Figure F).
- Check for air bubbles and proceed to Step 7 for instructions on how to remove air bubbles.

Figure F

Step 7: Remove air bubbles and adjust to the prescribed dose (mL).

- Hold the syringe and tap the sides to send bubbles to the tip.
- With the syringe attached to the bottle, push the plunger up to remove the air bubbles from the top (see Figure G).
- After the bubbles are removed, push the plunger up until the top of the colored plunger is even with the markings on the syringe for the prescribed dose.

Figure G

Air bubbles must be removed to ensure the correct dose.

Note: Repeat steps 6 and 7 if any air bubbles remain.

Step 8: Remove the syringe from the bottle.

- Turn the assembled bottle upright.
- Hold the middle of the syringe and carefully remove it from the bottle (see Figure H).
- Place the bottle aside.

Figure H

Do not touch the plunger of the syringe to avoid accidentally spilling the medicine before you are ready to take or give the dose.

Note: If more than 1 syringe is needed to take or give the full dose, repeat steps 5 to 8 with the second syringe to complete the prescribed dose.

Step 9: Take or give IMBRUVICA.

- Place the tip of the syringe along the inside of the cheek.
- Slowly push the plunger all the way in to take or give the entire dose (see Figure I).
- Repeat with second syringe if needed to complete the prescribed dose.

Note: IMBRUVICA must be taken or given as soon as possible after being drawn from the bottle.
Note: After swallowing the dose of medicine make sure to drink water.

Figure I

Step 10: Recap the bottle.

- Place the cap back on the IMBRUVICA bottle (see Figure J).
- Make sure the bottle is tightly closed between each use.

Figure J

Step 11: Rinse the syringe.

- Remove the plunger from the syringe.
- Rinse the plunger and the syringe only with water and air dry (see Figure K).
- Store the syringe in a clean, dry place.

Figure K

Do not clean the syringe with soap or in the dishwasher.

Turn over for more information

How to store IMBRUVICA Oral Suspension

- Store the bottle between 36°F and 77°F (2°C and 25°C).

Do not freeze.

- IMBRUVICA oral suspension comes in a bottle with a child-resistant cap.
- Store IMBRUVICA and all medications out of the reach of children.

How to dispose of IMBRUVICA

Throw away (dispose of) any unused medicine within 60 days after first opening of the bottle. At the same time, throw away any used or unused syringes.

- Ask your pharmacist how to properly dispose of the medicine.
- For syringe disposal, rinse and place in household trash.

This Instructions for Use has been approved by the U.S. Food and Drug Administration.

Distributed and Marketed by:
Pharmacyclics LLC
South San Francisco, CA 94080 USA
and
Marketed by:
Janssen Biotech, Inc.
Horsham, PA 19044 USA

Patent http://www.imbruvica.com
IMBRUVICA® and its design are trademarks of Pharmacyclics, LLC, an AbbVie company

© 2025 Pharmacyclics LLC. All rights reserved.

© 2025 Janssen Biotech, Inc. All rights reserved.

20096655

Revised: 10/2025

PACKAGE LABEL

PRINCIPAL DISPLAY PANEL - 28 Capsule Bottle Carton

NDC 57962-070-28

Imbruvica®
(ibrutinib) capsules

70 mg

Each capsule contains: ibrutinib 70 mg
Swallow capsules whole with water

28 Capsules

Rx Only

pharmacyclics®
An AbbVie Company

janssen

PACKAGE LABEL

PRINCIPAL DISPLAY PANEL - 90 Capsule Bottle Carton

NDC 57962-140-09

Imbruvica®
(ibrutinib) capsules

140 mg

Each capsule contains: ibrutinib 140 mg
Swallow capsules whole with water

90 Capsules

Rx Only

pharmacyclics®
An AbbVie Company

janssen

PACKAGE LABEL

PRINCIPAL DISPLAY PANEL - 28 Tablet Blister Carton

NDC 57962-014-28

Imbruvica®
(ibrutinib) tablets

140 mg per tablet

Each tablet contains ibrutinib 140 mg
Wallet card contains 28 tablets

Rx Only

pharmacyclics®
An AbbVie Company

janssen

PACKAGE LABEL

PRINCIPAL DISPLAY PANEL - 28 Tablet Blister Carton

NDC 57962-280-28

Imbruvica®
(ibrutinib) tablets

280 mg per tablet

Each tablet contains ibrutinib 280 mg
Wallet card contains 28 tablets

Rx Only

pharmacyclics®

An AbbVie Company

janssen

PACKAGE LABEL

PRINCIPAL DISPLAY PANEL - 28 Tablet Blister Carton

NDC 57962-420-28

Imbruvica®
(ibrutinib) tablets

420 mg per tablet

Each tablet contains ibrutinib 420 mg
Wallet card contains 28 tablets

Rx Only

pharmacyclics®
An AbbVie Company

janssen

PACKAGE LABEL

PRINCIPAL DISPLAY PANEL

NDC 57962-007-12

Imbruvica®
(ibrutinib)
Oral Suspension

70 mg/mL

For Oral Use Only
Shake well before each use
Discard after 60 Days

Rx Only

108mL per Bottle

pharmacyclics®
An AbbVie Company

janssen